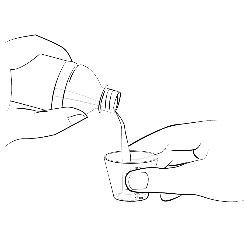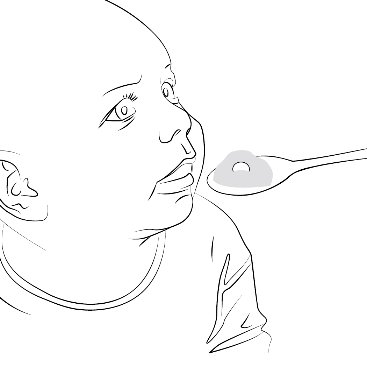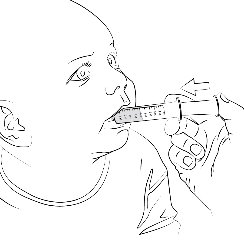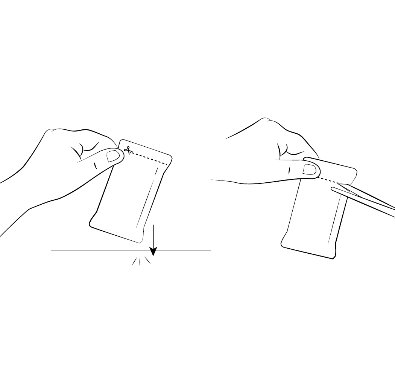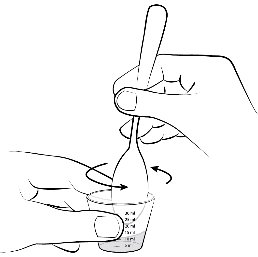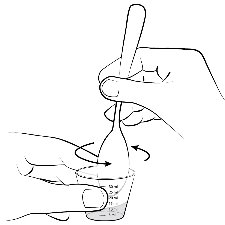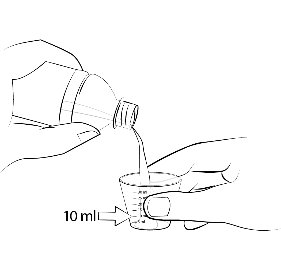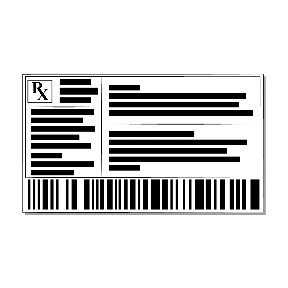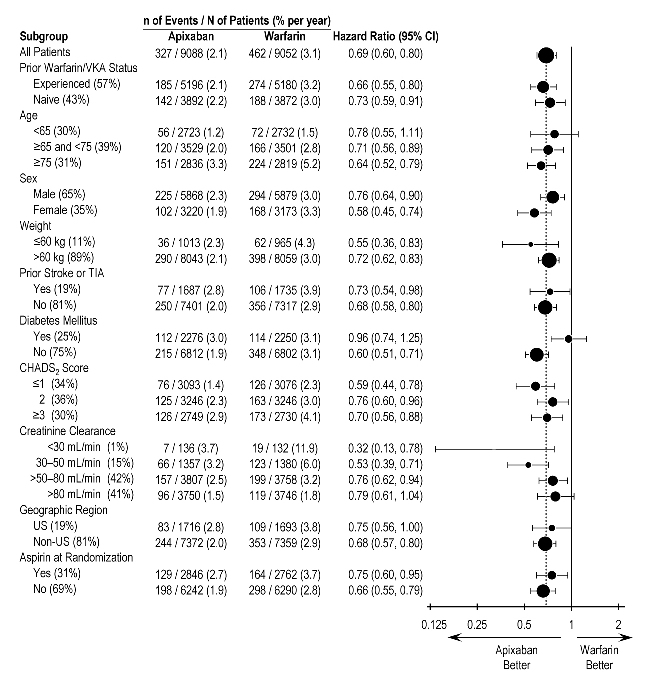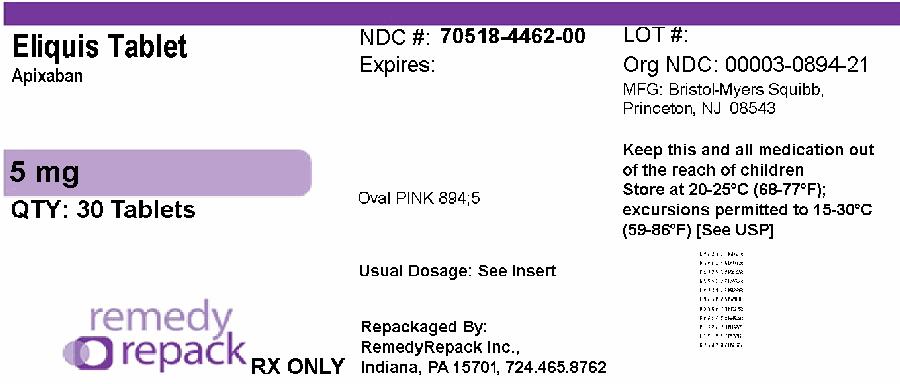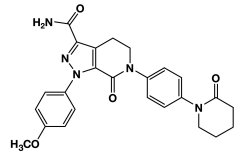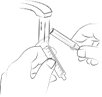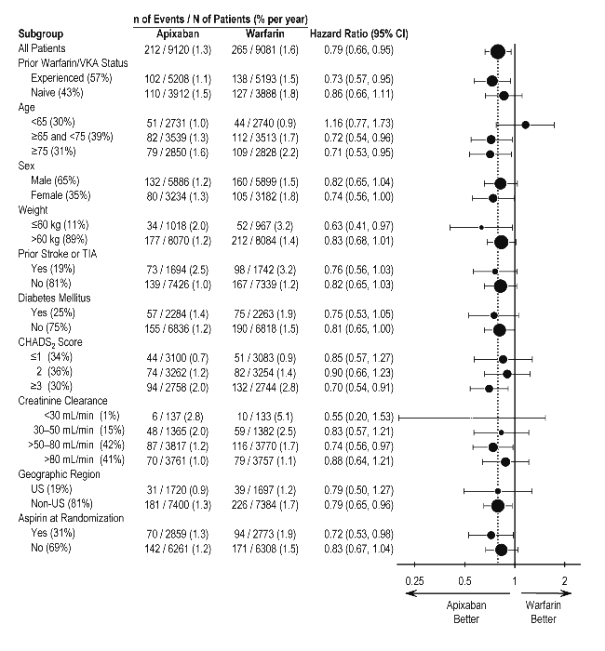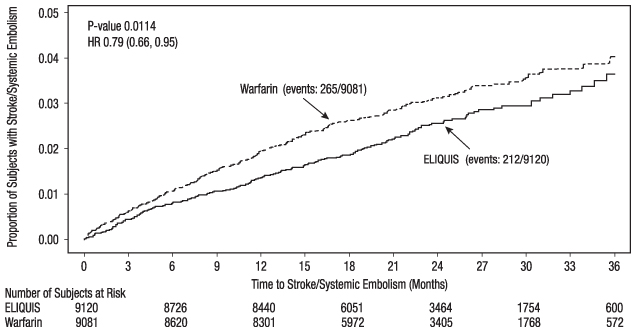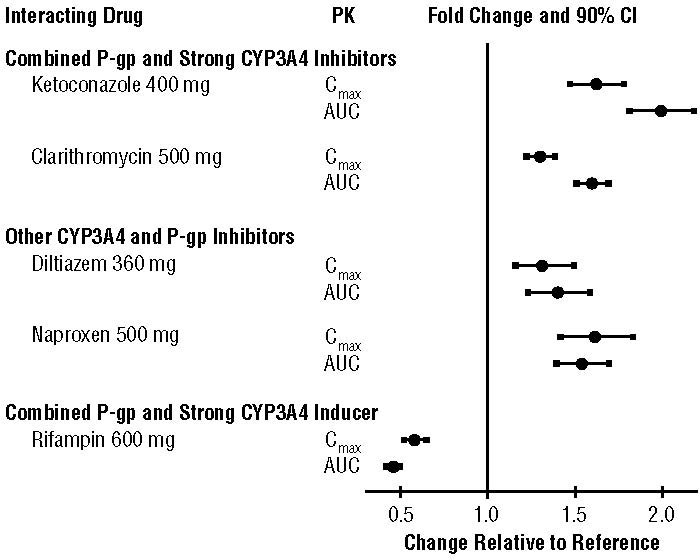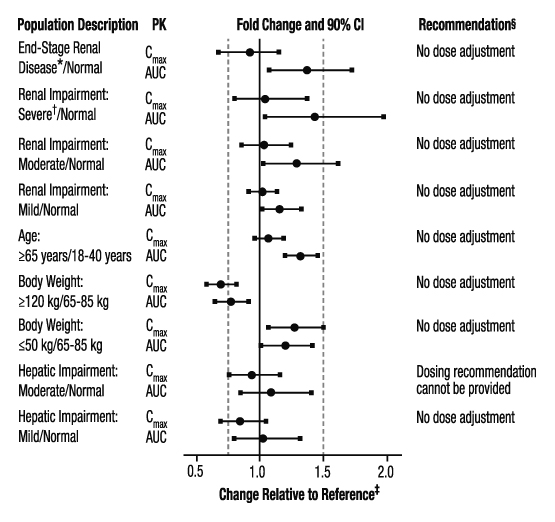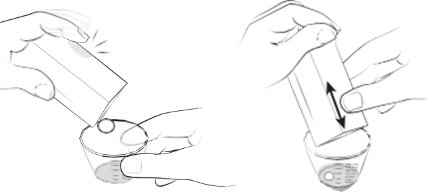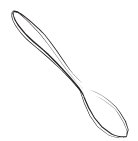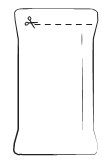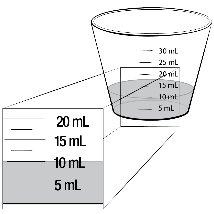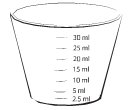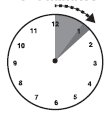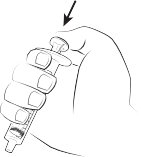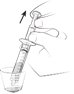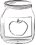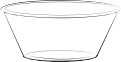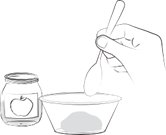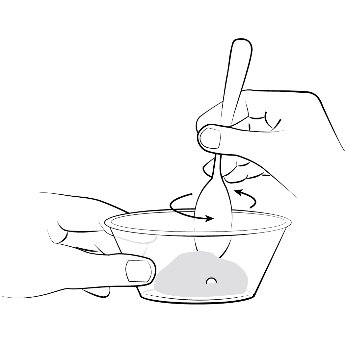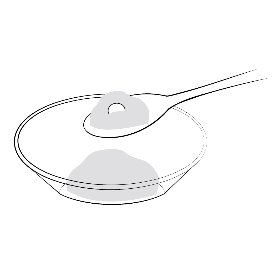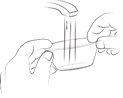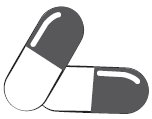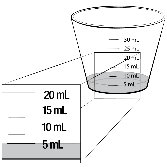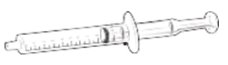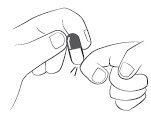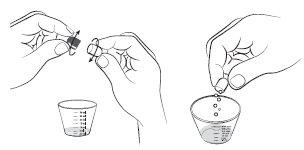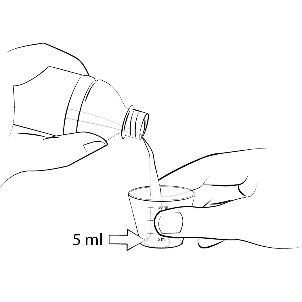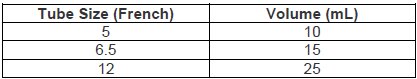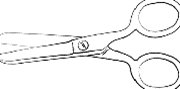 DRUG LABEL: ELIQUIS
NDC: 70518-4462 | Form: TABLET, FILM COATED
Manufacturer: REMEDYREPACK INC.
Category: prescription | Type: HUMAN PRESCRIPTION DRUG LABEL
Date: 20250829

ACTIVE INGREDIENTS: APIXABAN 5 mg/1 1
INACTIVE INGREDIENTS: ANHYDROUS LACTOSE; MICROCRYSTALLINE CELLULOSE; CROSCARMELLOSE SODIUM; SODIUM LAURYL SULFATE; MAGNESIUM STEARATE; LACTOSE MONOHYDRATE; HYPROMELLOSE, UNSPECIFIED; TITANIUM DIOXIDE; TRIACETIN; FERRIC OXIDE RED

HIGHLIGHTS OF PRESCRIBING INFORMATION

These highlights do not include all the information needed to use ELIQUIS safely and effectively. See full prescribing information for ELIQUIS.
ELIQUIS®(apixaban) tablets, for oral use
ELIQUIS®(apixaban) tablets for oral suspension
ELIQUIS®SPRINKLE (apixaban) for oral suspension
Initial U.S. Approval: 2012

RECENT MAJOR CHANGES

Indications and Usage (1.6) | 04/2025
Dosage and Administration (2.2, 2.6, 2.7) | 04/2025
Warnings and Precautions (5.2, 5.3) | 04/2025

WARNING: (A) PREMATURE DISCONTINUATION OF ELIQUIS INCREASES THE RISK OF THROMBOTIC EVENTS (B) SPINAL/EPIDURAL HEMATOMA

WARNING: (A) PREMATURE DISCONTINUATION OF ELIQUIS INCREASES THE RISK OF THROMBOTIC EVENTS
(B) SPINAL/EPIDURAL HEMATOMA

See full prescribing information for complete boxed warning.

(A) PREMATURE DISCONTINUATION OF ELIQUIS INCREASES THE RISK OF THROMBOTIC EVENTS: Premature discontinuation of any oral anticoagulant, including ELIQUIS, increases the risk of thrombotic events. To reduce this risk, consider coverage with another anticoagulant if ELIQUIS is discontinued for a reason other than pathological bleeding or completion of a course of therapy. (2.5, 5.1, 14.1)

(B) SPINAL/EPIDURAL HEMATOMA: Epidural or spinal hematomas may occur in patients treated with ELIQUIS who are receiving neuraxial anesthesia or undergoing spinal puncture. These hematomas may result in long-term or permanent paralysis. Consider these risks when scheduling patients for spinal procedures. (5.3)

1 INDICATIONS AND USAGE

ELIQUIS is a factor Xa inhibitor indicated:

- to reduce the risk of stroke and systemic embolism in adult patients with nonvalvular atrial fibrillation. (1.1)
- for the prophylaxis of deep vein thrombosis (DVT), which may lead to pulmonary embolism (PE), in adult patients who have undergone hip or knee replacement surgery. (1.2)
- for the treatment of DVT and PE, and for the reduction in the risk of recurrent DVT and PE in adult patients following initial therapy. (1.3, 1.4, 1.5)
- Treatment of venous thromboembolism (VTE) and reduction in the risk of recurrent VTE in pediatric patients from birth and older after at least 5 days of initial anticoagulant treatment. (1.6)

2 DOSAGE AND ADMINISTRATION

- Reduction of risk of stroke and systemic embolism in nonvalvular atrial fibrillation:
  - The recommended dose is 5 mg orally twice daily. (2.1)
  - In patients with at least 2 of the following characteristics: age greater than or equal to 80 years, body weight less than or equal to 60 kg, or serum creatinine greater than or equal to 1.5 mg/dL, the recommended dose is 2.5 mg orally twice daily. (2.1)
- Prophylaxis of DVT following hip or knee replacement surgery:
  - The recommended dose is 2.5 mg orally twice daily. (2.1)
- Treatment of DVT and PE:
  - The recommended dose is 10 mg taken orally twice daily for 7 days, followed by 5 mg taken orally twice daily. (2.1)
- Reduction in the risk of recurrent DVT and PE following initial therapy:
  - The recommended dose is 2.5 mg taken orally twice daily. (2.1)
- Treatment of VTE and reduction in the risk of recurrent VTE in pediatric patients from birth and older after at least 5 days of initial anticoagulant treatment:
  - See dosing recommendations in the Full Prescribing Information (2.2)

3 DOSAGE FORMS AND STRENGTHS

- Tablets: 2.5 mg and 5 mg (3)
- Tablet For Oral Suspension: 0.5 mg (3)
- For Oral Suspension: 0.15 mg in a yellow opaque capsule (3)

4 CONTRAINDICATIONS

- Active pathological bleeding (4)
- Severe hypersensitivity to ELIQUIS (4)

5 WARNINGS AND PRECAUTIONS

- ELIQUIS can cause serious, potentially fatal, bleeding. Promptly evaluate signs and symptoms of blood loss. An agent to reverse the anti-factor Xa activity of apixaban is available. (5.2)
- Prosthetic heart valves: ELIQUIS use not recommended. (5.4)
- Increased Risk of Thrombosis in Patients with Triple Positive Antiphospholipid Syndrome: ELIQUIS use not recommended. (5.6)

6 ADVERSE REACTIONS

- Most common adverse reactions (>1%) in adult patients are related to bleeding. (6.1)
- The most common adverse reactions (≥10%) in pediatric patients were headache, vomiting, and excessive menstrual bleeding.(6.1)

To report SUSPECTED ADVERSE REACTIONS, contact Bristol-Myers Squibb at 1-800-721-5072 or FDA at 1-800-FDA-1088 or www.fda.gov/medwatch.

7 DRUG INTERACTIONS

- Combined P-gp and strong CYP3A4 inhibitors increase blood levels of apixaban. Reduce ELIQUIS dose or avoid coadministration. (2.6, 7.1, 12.3)
- Simultaneous use of combined P-gp and strong CYP3A4 inducers reduces blood levels of apixaban: Avoid concomitant use. (7.2, 12.3)

8 USE IN SPECIFIC POPULATIONS

- Pregnancy:Not recommended. (8.1)
- Lactation:Advise not to breastfeed. (8.2)
- Severe Hepatic Impairment:Not recommended. (8.7, 12.2)

FULL PRESCRIBING INFORMATION

WARNING: (A) PREMATURE DISCONTINUATION OF ELIQUIS INCREASES THE RISK OF THROMBOTIC EVENTS (B) SPINAL/EPIDURAL HEMATOMA

(A) PREMATURE DISCONTINUATION OF ELIQUIS INCREASES THE RISK OF THROMBOTIC EVENTS

Premature discontinuation of any oral anticoagulant, including ELIQUIS, increases the risk of thrombotic events. If anticoagulation with ELIQUIS is discontinued for a reason other than pathological bleeding or completion of a course of therapy, consider coverage with another anticoagulant [see Dosage and Administration (2.5), Warnings and Precautions (5.1), and Clinical Studies (14.1)] .

(B) SPINAL/EPIDURAL HEMATOMA

Epidural or spinal hematomas may occur in patients treated with ELIQUIS who are receiving neuraxial anesthesia or undergoing spinal puncture. These hematomas may result in long-term or permanent paralysis. Consider these risks when scheduling patients for spinal procedures. Factors that can increase the risk of developing epidural or spinal hematomas in these patients include:

- use of indwelling epidural catheters
- concomitant use of other drugs that affect hemostasis, such as nonsteroidal anti-inflammatory drugs (NSAIDs), platelet inhibitors, other anticoagulants
- a history of traumatic or repeated epidural or spinal punctures
- a history of spinal deformity or spinal surgery
- optimal timing between the administration of ELIQUIS and neuraxial procedures is not known

[see Warnings and Precautions (5.3)]

Monitor patients frequently for signs and symptoms of neurological impairment. If neurological compromise is noted, urgent treatment is necessary [see Warnings and Precautions (5.3)] .

Consider the benefits and risks before neuraxial intervention in patients anticoagulated or to be anticoagulated [see Warnings and Precautions (5.3)] .

1 INDICATIONS AND USAGE

1.1 Reduction of Risk of Stroke and Systemic Embolism in Nonvalvular Atrial Fibrillation

ELIQUIS is indicated to reduce the risk of stroke and systemic embolism in adult patients with nonvalvular atrial fibrillation.

1.2 Prophylaxis of Deep Vein Thrombosis Following Hip or Knee Replacement Surgery

ELIQUIS is indicated for the prophylaxis of deep vein thrombosis (DVT), which may lead to pulmonary embolism (PE), in adult patients who have undergone hip or knee replacement surgery.

1.3 Treatment of Deep Vein Thrombosis

ELIQUIS is indicated for the treatment of adults with deep vein thrombosis (DVT).

1.4 Treatment of Pulmonary Embolism

ELIQUIS is indicated for the treatment of adults with pulmonary embolism (PE).

1.5 Reduction in the Risk of Recurrence of Deep Vein Thrombosis and Pulmonary Embolism

ELIQUIS is indicated to reduce the risk of recurrent deep vein thrombosis (DVT) and pulmonary embolism (PE) in adult patients following initial therapy.

1.6 Treatment of Venous Thromboembolism and Reduction in the Risk of Recurrent Venous Thromboembolism in Pediatric Patients

ELIQUIS is indicated for the treatment of venous thromboembolism (VTE) and reduction in the risk of recurrent VTE in pediatric patients from birth and older after at least 5 days of initial anticoagulant treatment.

2 DOSAGE AND ADMINISTRATION

2.1 Recommended Dose in Adult Patients

Reduction of Risk of Stroke and Systemic Embolism in Patients with Nonvalvular Atrial Fibrillation

The recommended dose of ELIQUIS for most patients is 5 mg taken orally twice daily.

The recommended dose of ELIQUIS is 2.5 mg twice daily in patients with at least two of the following characteristics:

- age greater than or equal to 80 years
- body weight less than or equal to 60 kg
- serum creatinine greater than or equal to 1.5 mg/dL

Prophylaxis of Deep Vein Thrombosis Following Hip or Knee Replacement Surgery

The recommended dose of ELIQUIS is 2.5 mg taken orally twice daily. The initial dose should be taken 12 to 24 hours after surgery.

- In patients undergoing hip replacement surgery, the recommended duration of treatment is 35 days.
- In patients undergoing knee replacement surgery, the recommended duration of treatment is 12 days.

Treatment of DVT and PE

The recommended dose of ELIQUIS is 10 mg taken orally twice daily for the first 7 days of therapy. After 7 days, the recommended dose is 5 mg taken orally twice daily.

Reduction in the Risk of Recurrence of DVT and PE

The recommended dose of ELIQUIS is 2.5 mg taken orally twice daily after at least 6 months of treatment for DVT or PE [see Clinical Studies (14.3)] .

2.2 Recommended Dose in Pediatric Patients

Treatment of Venous Thromboembolism (VTE) and Reduction in the Risk of Recurrent VTE in Pediatric Patients

The recommended dose of ELIQUIS is based on the patient’s weight, see Table 1. Adjust the dose according to weight-tier as treatment progresses. Initiate ELIQUIS treatment for pediatric patients from birth to less than 18 years of age following at least 5 days of initial anticoagulation therapy. Individualize duration of overall therapy after careful assessment of the treatment benefit and the risk for bleeding.

Table 1: Dose Recommendation in Pediatric Patients from Birth to less than 18 Years of Age for the Treatment of VTE and Reduction in the Risk of Recurrent VTE

 |  | Days 1-7 | Days 8 and beyond
Presentation | Body weight; (kg) | Dosing schedule | Dosing schedule
Powder in Capsule 0.15 mg; For pediatric use | 2.6 to less than 4 | 0.3 mg twice daily | 0.15 mg twice daily
Tablet 0.5 mg; For pediatric use | 4 to less than 6 | 1 mg twice daily | 0.5 mg twice daily
Tablet 0.5 mg; For pediatric use | 6 to less than 9 | 2 mg twice daily | 1 mg twice daily
Tablet 0.5 mg; For pediatric use | 9 to less than 12 | 3 mg twice daily | 1.5 mg twice daily
Tablet 0.5 mg; For pediatric use | 12 to less than 18 | 4 mg twice daily | 2 mg twice daily
Tablet 0.5 mg; For pediatric use | 18 to less than 25 | 6 mg twice daily | 3 mg twice daily
Tablet 0.5 mg; For pediatric use | 25 to less than 35 | 8 mg twice daily | 4 mg twice daily
Tablets 2.5 mg and 5 mg | greater than or equal to 35 | 10 mg twice daily | 5 mg twice daily

ELIQUIS is not recommended for use in pediatric patients less than 2.6 kg because ELIQUIS was not studied in these patients.

2.3 Missed Dose

If a dose of ELIQUIS is not taken at the scheduled time, the dose should be taken as soon as possible on the same day and twice-daily administration should be resumed. The dose should not be doubled to make up for a missed dose.

2.4 Temporary Interruption for Surgery and Other Interventions

ELIQUIS should be discontinued at least 48 hours prior to elective surgery or invasive procedures with a moderate or high risk of unacceptable or clinically significant bleeding [see Warnings and Precautions (5.2)] . ELIQUIS should be discontinued at least 24 hours prior to elective surgery or invasive procedures with a low risk of bleeding or where the bleeding would be non-critical in location and easily controlled. Bridging anticoagulation during the 24 to 48 hours after stopping ELIQUIS and prior to the intervention is not generally required. ELIQUIS should be restarted after the surgical or other procedures as soon as adequate hemostasis has been established.

2.5 Converting from or to ELIQUIS

Switching from warfarin to ELIQUIS:Warfarin should be discontinued and ELIQUIS started when the international normalized ratio (INR) is below 2.0.

Switching from ELIQUIS to warfarin:ELIQUIS affects INR, so that initial INR measurements during the transition to warfarin may not be useful for determining the appropriate dose of warfarin. One approach is to discontinue ELIQUIS and begin both a parenteral anticoagulant and warfarin at the time the next dose of ELIQUIS would have been taken, discontinuing the parenteral anticoagulant when INR reaches an acceptable range.

Switching from ELIQUIS to anticoagulants other than warfarin (oral or parenteral):Discontinue ELIQUIS and begin taking the new anticoagulant other than warfarin at the usual time of the next dose of ELIQUIS.

Switching from anticoagulants other than warfarin (oral or parenteral) to ELIQUIS:Discontinue the anticoagulant other than warfarin and begin taking ELIQUIS at the usual time of the next dose of the anticoagulant other than warfarin.

2.6 Combined P-gp and Strong CYP3A4 Inhibitors

For adult patients receiving ELIQUIS doses of 5 mg or 10 mg twice daily, reduce the dose by 50% when ELIQUIS is coadministered with drugs that are combined P-glycoprotein (P-gp) and strong cytochrome P450 3A4 (CYP3A4) inhibitors (e.g., ketoconazole, itraconazole, ritonavir) [see Clinical Pharmacology (12.3)] .

In patients already taking 2.5 mg twice daily, avoid coadministration of ELIQUIS with combined P-gp and strong CYP3A4 inhibitors [see Drug Interactions (7.1)].

2.7 Administration Options

Adult and pediatric patients weighing greater than or equal to 35 kg.

For patients who are unable to swallow whole tablets, 5 mg and 2.5 mg ELIQUIS tablets may be crushed and suspended in water, 5% dextrose in water (D5W), or apple juice, or mixed with applesauce and promptly administered orally [see Clinical Pharmacology (12.3)] . Alternatively, ELIQUIS tablets may be crushed and suspended in 60 mL of water or D5W and promptly delivered through a 12 French nasogastric tube [see Clinical Pharmacology (12.3)] .

Following administration of the dose, the nasogastric tube should be flushed with an additional 20 mL of water or D5W.

Crushed ELIQUIS tablets are stable in water, D5W, apple juice, and applesauce for up to 4 hours.

Pediatric patients weighing less than 35 kg.

Capsules

The 0.15 mg ELIQUIS SPRINKLE capsule must be opened, and the entire contents sprinkled in water or infant formula, mixed, and administered as described in the Instructions for Use (IFU). The liquid mixtures should be administered within 2 hours. Do not swallow capsule.

Tablets for oral suspension

The 0.5 mg ELIQUIS tablet in a packet for oral suspension should be mixed with water, infant formula, apple juice, or apple sauce as described in the IFU. The liquid mixtures with water, infant formula or apple juice should be administered within 2 hours and the mixture in apple sauce should be administered immediately. Each packet is for single use only. For pediatric patients who have difficulty swallowing, the liquid mixture can be delivered through a 5 French, 6.5 French or 12 French nasogastric tube or gastrostomy tube. See IFU.

3 DOSAGE FORMS AND STRENGTHS

- 0.5 mg, pink, round, film-coated tablets for oral suspension packaged in packets.
  1-count (0.5 mg), 3-count (1.5 mg), and 4-count (2 mg).
- 2.5 mg, yellow, round, biconvex, film-coated tablets with “893” debossed on one side and “2½” on the other side.
- 5 mg, pink, oval-shaped, biconvex, film-coated tablets with “894” debossed on one side and “5” on the other side.
- 0.15 mg, white to pale yellow powder for oral suspension, in a yellow opaque capsule marked “898”.

4 CONTRAINDICATIONS

ELIQUIS is contraindicated in patients with the following conditions:

- Active pathological bleeding [see Warnings and Precautions (5.2)and Adverse Reactions (6.1)]
- Severe hypersensitivity reaction to ELIQUIS (e.g., anaphylactic reactions) [see Adverse Reactions (6.1)]

5 WARNINGS AND PRECAUTIONS

5.1 Increased Risk of Thrombotic Events after Premature Discontinuation

Premature discontinuation of any oral anticoagulant, including ELIQUIS, in the absence of adequate alternative anticoagulation increases the risk of thrombotic events. An increased rate of stroke was observed during the transition from ELIQUIS to warfarin in clinical trials in atrial fibrillation patients. If ELIQUIS is discontinued for a reason other than pathological bleeding or completion of a course of therapy, consider coverage with another anticoagulant [see Dosage and Administration (2.5) and Clinical Studies (14.1)] .

5.2 Bleeding

ELIQUIS increases the risk of bleeding and can cause serious, potentially fatal, bleeding [see Dosage and Administration (2.1) and Adverse Reactions (6.1)] .

Concomitant use of drugs affecting hemostasis increases the risk of bleeding. These include aspirin and other antiplatelet agents, other anticoagulants, heparin, thrombolytic agents, selective serotonin reuptake inhibitors, serotonin norepinephrine reuptake inhibitors, and nonsteroidal anti-inflammatory drugs (NSAIDs) [see Drug Interactions (7.3)] .

Advise patients of signs and symptoms of blood loss and to report them immediately or go to an emergency room. Discontinue ELIQUIS in patients with active pathological hemorrhage.

Reversal of Anticoagulant Effect

A specific reversal agent (andexanet alfa) antagonizing the pharmacodynamic effect of apixaban is available for adults. However, its safety and efficacy have not been established in pediatric patients (refer to the USPI of andexanet alfa).The pharmacodynamic effect of ELIQUIS can be expected to persist for at least 24 hours after the last dose, i.e., for about two drug half-lives. Prothrombin complex concentrate (PCC), activated prothrombin complex concentrate or recombinant factor VIIa may be considered, but have not been evaluated in clinical studies [see Clinical Pharmacology (12.2)] . When PCCs are used, monitoring for the anticoagulation effect of apixaban using a clotting test (PT, INR, or aPTT) or anti-factor Xa (FXa) activity is not useful and is not recommended. Activated oral charcoal reduces absorption of apixaban, thereby lowering apixaban plasma concentration [see Overdosage (10)].

Hemodialysis does not appear to have a substantial impact on apixaban exposure [see Clinical Pharmacology (12.3)] . Protamine sulfate and vitamin K are not expected to affect the anticoagulant activity of apixaban. There is no experience with antifibrinolytic agents (tranexamic acid, aminocaproic acid) in individuals receiving apixaban. There is no experience with systemic hemostatics (desmopressin) in individuals receiving ELIQUIS, and they are not expected to be effective as a reversal agent.

5.3 Spinal/Epidural Anesthesia or Puncture

When neuraxial anesthesia (spinal/epidural anesthesia) or spinal/epidural puncture is employed, patients treated with antithrombotic agents for prevention of thromboembolic complications are at risk of developing an epidural or spinal hematoma which can result in long-term or permanent paralysis.

The risk of these events may be increased by the postoperative use of indwelling epidural catheters or the concomitant use of medicinal products affecting hemostasis. Indwelling epidural or intrathecal catheters should not be removed earlier than 24 hours after the last administration of ELIQUIS. The next dose of ELIQUIS should not be administered earlier than 5 hours after the removal of the catheter. The risk may also be increased by traumatic or repeated epidural or spinal puncture. If traumatic puncture occurs, delay the administration of ELIQUIS for 48 hours.

Monitor patients frequently for signs and symptoms of neurological impairment (e.g., numbness or weakness of the legs, or bowel or bladder dysfunction). If neurological compromise is noted, urgent diagnosis and treatment is necessary. Prior to neuraxial intervention the physician should consider the potential benefit versus the risk in anticoagulated patients or in patients to be anticoagulated for thromboprophylaxis.

No data are available on the timing of the placement or removal of neuraxial catheters in pediatric patients while on ELIQUIS. In such cases, discontinue ELIQUIS and consider a short acting parenteral anticoagulant.

5.4 Patients with Prosthetic Heart Valves

The safety and efficacy of ELIQUIS have not been studied in patients with prosthetic heart valves. Therefore, use of ELIQUIS is not recommended in these patients.

5.5 Acute PE in Hemodynamically Unstable Patients or Patients who Require Thrombolysis or Pulmonary Embolectomy

Initiation of ELIQUIS is not recommended as an alternative to unfractionated heparin for the initial treatment of patients with PE who present with hemodynamic instability or who may receive thrombolysis or pulmonary embolectomy.

5.6 Increased Risk of Thrombosis in Patients with Triple Positive Antiphospholipid Syndrome

Direct-acting oral anticoagulants (DOACs), including ELIQUIS, are not recommended for use in patients with triple-positive antiphospholipid syndrome (APS). For patients with APS (especially those who are triple positive [positive for lupus anticoagulant, anticardiolipin, and anti-beta 2-glycoprotein I antibodies]), treatment with DOACs has been associated with increased rates of recurrent thrombotic events compared with vitamin K antagonist therapy.

6 ADVERSE REACTIONS

The following clinically significant adverse reactions are discussed in greater detail in other sections of the prescribing information.

- Increased Risk of Thrombotic Events After Premature Discontinuation [see Warnings and Precautions (5.1)]
- Bleeding [see Warnings and Precautions (5.2)]
- Spinal/Epidural Anesthesia or Puncture [see Warnings and Precautions (5.3)]

6.1 Clinical Trials Experience

Adult Patients

Because clinical trials are conducted under widely varying conditions, adverse reaction rates observed in the clinical trials of a drug cannot be directly compared to rates in the clinical trials of another drug and may not reflect the rates observed in practice.

Reduction of Risk of Stroke and Systemic Embolism in Patients with Nonvalvular Atrial Fibrillation

The safety of ELIQUIS was evaluated in the ARISTOTLE and AVERROES studies [see Clinical Studies (14)] , including 11,284 patients exposed to ELIQUIS 5 mg twice daily and 602 patients exposed to ELIQUIS 2.5 mg twice daily. The duration of ELIQUIS exposure was ≥12 months for 9375 patients and ≥24 months for 3369 patients in the two studies. In ARISTOTLE, the mean duration of exposure was 89 weeks (>15,000 patient-years). In AVERROES, the mean duration of exposure was approximately 59 weeks (>3000 patient-years).

The most common reason for treatment discontinuation in both studies was for bleeding-related adverse reactions; in ARISTOTLE this occurred in 1.7% and 2.5% of patients treated with ELIQUIS and warfarin, respectively, and in AVERROES, in 1.5% and 1.3% on ELIQUIS and aspirin, respectively.

Bleeding in Patients with Nonvalvular Atrial Fibrillation in ARISTOTLE and AVERROES

Tables 2 and 3 show the number of patients experiencing major bleeding during the treatment period and the bleeding rate (percentage of subjects with at least one bleeding event per 100 patient-years) in ARISTOTLE and AVERROES.

Table 2: Bleeding Events in Patients with Nonvalvular Atrial Fibrillation in ARISTOTLE*
 | ELIQUIS N=9088 n (per 100 pt-year) | Warfarin N=9052 n (per 100 pt-year) | Hazard Ratio (95% CI) | P-value
Major† | 327 (2.13) | 462 (3.09) | 0.69 (0.60, 0.80) | <0.0001
Intracranial (ICH)‡ | 52 (0.33) | 125 (0.82) | 0.41 (0.30, 0.57) | -
Hemorrhagic stroke§ | 38 (0.24) | 74 (0.49) | 0.51 (0.34, 0.75) | -
Other ICH | 15 (0.10) | 51 (0.34) | 0.29 (0.16, 0.51) | -
Gastrointestinal (GI)¶ | 128 (0.83) | 141 (0.93) | 0.89 (0.70, 1.14) | -
Fatal** | 10 (0.06) | 37 (0.24) | 0.27 (0.13, 0.53) | -
Intracranial | 4 (0.03) | 30 (0.20) | 0.13 (0.05, 0.37) | -
Non-intracranial | 6 (0.04) | 7 (0.05) | 0.84 (0.28, 2.15) | -
* Bleeding events within each subcategory were counted once per subject, but subjects may have contributed events to multiple endpoints. Bleeding events were counted during treatment or within 2 days of stopping study treatment (on-treatment period).
†Defined as clinically overt bleeding accompanied by one or more of the following: a decrease in hemoglobin of ≥2 g/dL, a transfusion of 2 or more units of packed red blood cells, bleeding at a critical site: intracranial, intraspinal, intraocular, pericardial, intra-articular, intramuscular with compartment syndrome, retroperitoneal or with fatal outcome.
‡Intracranial bleed includes intracerebral, intraventricular, subdural, and subarachnoid bleeding. Any type of hemorrhagic stroke was adjudicated and counted as an intracranial major bleed.
§On-treatment analysis based on the safety population, compared to ITT analysis presented in Section 14.
¶GI bleed includes upper GI, lower GI, and rectal bleeding.
** Fatal bleeding is an adjudicated death with the primary cause of death as intracranial bleeding or non-intracranial bleeding during the on-treatment period.

In ARISTOTLE, the results for major bleeding were generally consistent across most major subgroups including age, weight, CHADS2score (a scale from 0 to 6 used to estimate risk of stroke, with higher scores predicting greater risk), prior warfarin use, geographic region, and aspirin use at randomization (Figure 1). Subjects treated with ELIQUIS with diabetes bled more (3% per year) than did subjects without diabetes (1.9% per year).

Figure 1: Major Bleeding Hazard Ratios by Baseline Characteristics – ARISTOTLE Study

Note: The figure above presents effects in various subgroups, all of which are baseline characteristics and all of which were prespecified, if not the groupings. The 95% confidence limits that are shown do not take into account how many comparisons were made, nor do they reflect the effect of a particular factor after adjustment for all other factors. Apparent homogeneity or heterogeneity among groups should not be over-interpreted.

Table 3: Bleeding Events in Patients with Nonvalvular Atrial Fibrillation in AVERROES
 | ELIQUIS N=2798 n (%/year) | Aspirin N=2780 n (%/year) | Hazard Ratio (95% CI) | P-value
Major | 45 (1.41) | 29 (0.92) | 1.54 (0.96, 2.45) | 0.07
Fatal | 5 (0.16) | 5 (0.16) | 0.99 (0.23, 4.29) | -
Intracranial | 11 (0.34) | 11 (0.35) | 0.99 (0.39, 2.51) | -

Events associated with each endpoint were counted once per subject, but subjects may have contributed events to multiple endpoints.

Other Adverse Reactions

Hypersensitivity reactions (including drug hypersensitivity, such as skin rash, and anaphylactic reactions, such as allergic edema) and syncope were reported in <1% of patients receiving ELIQUIS.

Prophylaxis of Deep Vein Thrombosis Following Hip or Knee Replacement Surgery

The safety of ELIQUIS has been evaluated in 1 Phase II and 3 Phase III studies including 5924 patients exposed to ELIQUIS 2.5 mg twice daily undergoing major orthopedic surgery of the lower limbs (elective hip replacement or elective knee replacement) treated for up to 38 days.

In total, 11% of the patients treated with ELIQUIS 2.5 mg twice daily experienced adverse reactions.

Bleeding results during the treatment period in the Phase III studies are shown in Table 4. Bleeding was assessed in each study beginning with the first dose of double-blind study drug.

Table 4: Bleeding During the Treatment Period in Patients Undergoing Elective Hip or Knee Replacement Surgery
Bleeding Endpoint* | ADVANCE-3 Hip Replacement Surgery |  | ADVANCE-2 Knee Replacement Surgery |  | ADVANCE-1 Knee Replacement Surgery
 | ELIQUIS 2.5 mg po bid 35±3 days | Enoxaparin 40 mg sc qd 35±3 days | ELIQUIS 2.5 mg po bid 12±2 days | Enoxaparin 40 mg sc qd 12±2 days | ELIQUIS 2.5 mg po bid 12±2 days | Enoxaparin 30 mg sc q12h 12±2 days
 | First dose 12 to 24 hours post surgery | First dose 9 to 15 hours prior to surgery | First dose 12 to 24 hours post surgery | First dose 9 to 15 hours prior to surgery | First dose 12 to 24 hours post surgery | First dose 12 to 24 hours post surgery
All treated | N=2673 | N=2659 | N=1501 | N=1508 | N=1596 | N=1588
Major (including surgical site) | 22 (0.82%)† | 18 (0.68%) | 9 (0.60%)‡ | 14 (0.93%) | 11 (0.69%) | 22 (1.39%)
Fatal | 0 | 0 | 0 | 0 | 0 | 1 (0.06%)
Hgb decrease ≥2 g/dL | 13 (0.49%) | 10 (0.38%) | 8 (0.53%) | 9 (0.60%) | 10 (0.63%) | 16 (1.01%)
Transfusion of ≥2 units RBC | 16 (0.60%) | 14 (0.53%) | 5 (0.33%) | 9 (0.60%) | 9 (0.56%) | 18 (1.13%)
Bleed at critical site§ | 1 (0.04%) | 1 (0.04%) | 1 (0.07%) | 2 (0.13%) | 1 (0.06%) | 4 (0.25%)
Major + CRNM¶ | 129 (4.83%) | 134 (5.04%) | 53 (3.53%) | 72 (4.77%) | 46 (2.88%) | 68 (4.28%)
All | 313 (11.71%) | 334 (12.56%) | 104 (6.93%) | 126 (8.36%) | 85 (5.33%) | 108 (6.80%)
* All bleeding criteria included surgical site bleeding.
†Includes 13 subjects with major bleeding events that occurred before the first dose of ELIQUIS (administered 12 to 24 hours post surgery).
‡Includes 5 subjects with major bleeding events that occurred before the first dose of ELIQUIS (administered 12 to 24 hours post surgery).
§Intracranial, intraspinal, intraocular, pericardial, an operated joint requiring re-operation or intervention, intramuscular with compartment syndrome, or retroperitoneal. Bleeding into an operated joint requiring re-operation or intervention was present in all patients with this category of bleeding. Events and event rates include one enoxaparin-treated patient in ADVANCE-1 who also had intracranial hemorrhage.
¶CRNM = clinically relevant nonmajor.

Adverse reactions occurring in ≥1% of patients undergoing hip or knee replacement surgery in the 1 Phase II study and the 3 Phase III studies are listed in Table 5.

Table 5: Adverse Reactions Occurring in ≥1% of Patients in Either Group Undergoing Hip or Knee Replacement Surgery
 | ELIQUIS, n (%) 2.5 mg po bid N=5924 | Enoxaparin, n (%) 40 mg sc qd or 30 mg sc q12h N=5904
Nausea | 153 (2.6) | 159 (2.7)
Anemia (including postoperative and hemorrhagic anemia, and respective laboratory parameters) | 153 (2.6) | 178 (3.0)
Contusion | 83 (1.4) | 115 (1.9)
Hemorrhage (including hematoma, and vaginal and urethral hemorrhage) | 67 (1.1) | 81 (1.4)
Postprocedural hemorrhage (including postprocedural hematoma, wound hemorrhage, vessel puncture-site hematoma, and catheter-site hemorrhage) | 54 (0.9) | 60 (1.0)
Transaminases increased (including alanine aminotransferase increased and alanine aminotransferase abnormal) | 50 (0.8) | 71 (1.2)
Aspartate aminotransferase increased | 47 (0.8) | 69 (1.2)
Gamma-glutamyltransferase increased | 38 (0.6) | 65 (1.1)

Less common adverse reactions in ELIQUIS-treated patients undergoing hip or knee replacement surgery occurring at a frequency of ≥0.1% to <1%:

Blood and lymphatic system disorders:thrombocytopenia (including platelet count decreases)

Vascular disorders:hypotension (including procedural hypotension)

Respiratory, thoracic, and mediastinal disorders:epistaxis

Gastrointestinal disorders:gastrointestinal hemorrhage (including hematemesis and melena), hematochezia

Hepatobiliary disorders:liver function test abnormal, blood alkaline phosphatase increased, blood bilirubin increased

Renal and urinary disorders:hematuria (including respective laboratory parameters)

Injury, poisoning, and procedural complications:wound secretion, incision-site hemorrhage (including incision-site hematoma), operative hemorrhage

Less common adverse reactions in ELIQUIS-treated patients undergoing hip or knee replacement surgery occurring at a frequency of <0.1%:

Gingival bleeding, hemoptysis, hypersensitivity, muscle hemorrhage, ocular hemorrhage (including conjunctival hemorrhage), rectal hemorrhage

Treatment of DVT and PE and Reduction in the Risk of Recurrence of DVT or PE

The safety of ELIQUIS has been evaluated in the AMPLIFY and AMPLIFY-EXT studies, including 2676 patients exposed to ELIQUIS 10 mg twice daily, 3359 patients exposed to ELIQUIS 5 mg twice daily, and 840 patients exposed to ELIQUIS 2.5 mg twice daily.

Common adverse reactions (≥1%) were gingival bleeding, epistaxis, contusion, hematuria, rectal hemorrhage, hematoma, menorrhagia, and hemoptysis.

AMPLIFY Study

The mean duration of exposure to ELIQUIS was 154 days and to enoxaparin/warfarin was 152 days in the AMPLIFY study. Adverse reactions related to bleeding occurred in 417 (15.6%) ELIQUIS-treated patients compared to 661 (24.6%) enoxaparin/warfarin-treated patients. The discontinuation rate due to bleeding events was 0.7% in the ELIQUIS-treated patients compared to 1.7% in enoxaparin/warfarin-treated patients in the AMPLIFY study.

In the AMPLIFY study, ELIQUIS was statistically superior to enoxaparin/warfarin in the primary safety endpoint of major bleeding (relative risk 0.31, 95% CI [0.17, 0.55], P-value <0.0001).

Bleeding results from the AMPLIFY study are summarized in Table 6.

Table 6: Bleeding Results in the AMPLIFY Study
 | ELIQUIS N=2676 n (%) | Enoxaparin/Warfarin N=2689 n (%) | Relative Risk (95% CI)
Major | 15 (0.6) | 49 (1.8) | 0.31 (0.17, 0.55) p<0.0001
CRNM* | 103 (3.9) | 215 (8.0)
Major + CRNM | 115 (4.3) | 261 (9.7)
Minor | 313 (11.7) | 505 (18.8)
All | 402 (15.0) | 676 (25.1)
* CRNM = clinically relevant nonmajor bleeding.
Events associated with each endpoint were counted once per subject, but subjects may have contributed events to multiple endpoints.

Adverse reactions occurring in ≥1% of patients in the AMPLIFY study are listed in Table 7.

Table 7: Adverse Reactions Occurring in ≥1% of Patients Treated for DVT and PE in the AMPLIFY Study
 | ELIQUIS N=2676 n (%) | Enoxaparin/Warfarin N=2689 n (%)
Epistaxis | 77 (2.9) | 146 (5.4)
Contusion | 49 (1.8) | 97 (3.6)
Hematuria | 46 (1.7) | 102 (3.8)
Menorrhagia | 38 (1.4) | 30 (1.1)
Hematoma | 35 (1.3) | 76 (2.8)
Hemoptysis | 32 (1.2) | 31 (1.2)
Rectal hemorrhage | 26 (1.0) | 39 (1.5)
Gingival bleeding | 26 (1.0) | 50 (1.9)

AMPLIFY-EXT Study

The mean duration of exposure to ELIQUIS was approximately 330 days and to placebo was 312 days in the AMPLIFY-EXT study. Adverse reactions related to bleeding occurred in 219 (13.3%) ELIQUIS-treated patients compared to 72 (8.7%) placebo-treated patients. The discontinuation rate due to bleeding events was approximately 1% in the ELIQUIS-treated patients compared to 0.4% in those patients in the placebo group in the AMPLIFY-EXT study.

Bleeding results from the AMPLIFY-EXT study are summarized in Table 8.

Table 8: Bleeding Results in the AMPLIFY-EXT Study
 | ELIQUIS 2.5 mg bid N=840 n (%) | ELIQUIS 5 mg bid N=811 n (%) | Placebo N=826 n (%)
Major | 2 (0.2) | 1 (0.1) | 4 (0.5)
CRNM* | 25 (3.0) | 34 (4.2) | 19 (2.3)
Major + CRNM | 27 (3.2) | 35 (4.3) | 22 (2.7)
Minor | 75 (8.9) | 98 (12.1) | 58 (7.0)
All | 94 (11.2) | 121 (14.9) | 74 (9.0)
* CRNM = clinically relevant nonmajor bleeding.
Events associated with each endpoint were counted once per subject, but subjects may have contributed events to multiple endpoints.

Adverse reactions occurring in ≥1% of patients in the AMPLIFY-EXT study are listed in Table 9.

Table 9: Adverse Reactions Occurring in ≥1% of Patients Undergoing Extended Treatment for DVT and PE in the AMPLIFY-EXT Study
 | ELIQUIS 2.5 mg bid N=840 n (%) | ELIQUIS 5 mg bid N=811 n (%) | Placebo N=826 n (%)
Epistaxis | 13 (1.5) | 29 (3.6) | 9 (1.1)
Hematuria | 12 (1.4) | 17 (2.1) | 9 (1.1)
Hematoma | 13 (1.5) | 16 (2.0) | 10 (1.2)
Contusion | 18 (2.1) | 18 (2.2) | 18 (2.2)
Gingival bleeding | 12 (1.4) | 9 (1.1) | 3 (0.4)

Other Adverse Reactions

Less common adverse reactions in ELIQUIS-treated patients in the AMPLIFY or AMPLIFY-EXT studies occurring at a frequency of ≥0.1% to <1%:

Blood and lymphatic system disorders:hemorrhagic anemia

Gastrointestinal disorders:hematochezia, hemorrhoidal hemorrhage, gastrointestinal hemorrhage, hematemesis, melena, anal hemorrhage

Injury, poisoning, and procedural complications:wound hemorrhage, postprocedural hemorrhage, traumatic hematoma, periorbital hematoma

Musculoskeletal and connective tissue disorders:muscle hemorrhage

Reproductive system and breast disorders:vaginal hemorrhage, metrorrhagia, menometrorrhagia, genital hemorrhage

Vascular disorders:hemorrhage

Skin and subcutaneous tissue disorders:ecchymosis, skin hemorrhage, petechiae

Eye disorders:conjunctival hemorrhage, retinal hemorrhage, eye hemorrhage

Investigations:blood urine present, occult blood positive, occult blood, red blood cells urine positive

General disorders and administration-site conditions:injection-site hematoma, vessel puncture-site hematoma

Pediatric Patients

Treatment of Venous Thromboembolism (VTE) and Reduction in the Risk of Recurrent VTE in Pediatric Patients

The safety assessment of ELIQUIS is based on data from CV185325, a phase 3 study in 225 patients from birth and older. Patients were randomized 2:1 to receive body weight-adjusted doses of an age-appropriate formulation of ELIQUIS or standard of care. The standard of care treatments included unfractionated heparin (UFH), low molecular weight heparin (LMWH), or vitamin K antagonist (VKA).

Overall, the safety profile of ELIQUIS in pediatric patients from birth and older was generally similar to that in adults and consistent across different pediatric age groups. In pediatric patients, excessive menstrual bleeding occurred in 17 (11%) patients in the ELIQUIS group and 3 (4%) patients in the standard of care group. Epistaxis occurred in 24 (16%) patients in the ELIQUIS group and 14 (19%) patients in the standard of care group.

Bleeding results from Study CV185325 in pediatric patients with VTE are summarized in Table 10.

Table 10: Bleeding Results in Study CV185325 – Safety Analysis Set – Main Phase
 | ELIQUIS N=152 | Standard of care ** N=73
Major Bleeding
Number (%) Subjects with Event; 95% Confidence Interval (1) | 0 | 0
CRNM*
Number (%) Subjects with Event | 2 (1.3) | 1 (1.4)
95% Confidence Interval (1) | (0.2, 4.7) | (0.0, 7.4)
Minor Bleeding
Number (%) Subjects with Event | 54 (35.5) | 21 (28.8)
95% Confidence Interval (1) | (27.9, 43.7) | (18.8, 40.6)
All
Number (%) Subjects with Event | 55 (36.2) | 21 (28.8)
95% Confidence Interval (1) | (28.6, 44.4) | (18.8, 40.6)
* CRNM = clinically relevant nonmajor bleeding.
(1) 95% Confidence Interval calculated using the Clopper-Pearson exact method
Events associated with each endpoint were counted once per subject, but subjects may have contributed events to multiple endpoints.
** UFH/LMWH for patients less than 2 years of age and UFH/LMWH/VKA for those equal to or greater than 2 years of age.

Non-bleeding adverse reactions occurring in ≥10% of patients in study CV185325 are listed in Table 11.

Table 11: Other Adverse Reactions Occurring in ≥10% of Patients in Study CV185325
Number of Subjects Evaluable for Adverse Reaction | ELIQUIS N=152 n (%) | Standard of Care N=73 n (%)
Headache | 25 (16.4) | 11 (15.1)
Vomiting | 21 (13.8) | 5 (6.8)

7 DRUG INTERACTIONS

7.1 Combined P-gp and Strong CYP3A4 Inhibitors

For patients receiving ELIQUIS 5 mg or 10 mg twice daily, the dose of ELIQUIS should be decreased by 50% when coadministered with drugs that are combined P-gp and strong CYP3A4 inhibitors (e.g., ketoconazole, itraconazole, ritonavir) [see Dosage and Administration (2.6) and Clinical Pharmacology (12.3)] .

For patients receiving ELIQUIS at a dose of 2.5 mg twice daily, avoid coadministration with combined P-gp and strong CYP3A4 inhibitors [see Dosage and Administration (2.6) and Clinical Pharmacology (12.3)] .

Concomitant administration of combined P-gp and strong CYP3A4 inhibitors has not been studied in pediatric patients.

Apixaban is a substrate of both CYP3A4 and P-gp. Concomitant use with drugs that are combined P-gp and strong CYP3A4 inhibitors increases exposure to apixaban [see Clinical Pharmacology (12.3)] which increases the risk for bleeding.

Clarithromycin

Although clarithromycin is a combined P-gp and strong CYP3A4 inhibitor, pharmacokinetic data suggest that no dose adjustment is necessary with concomitant administration with ELIQUIS [see Clinical Pharmacology (12.3)] .

7.2 Combined P-gp and Strong CYP3A4 Inducers

Avoid concomitant use of ELIQUIS with combined P-gp and strong CYP3A4 inducers (e.g., rifampin, carbamazepine, phenytoin, St. John’s wort) because such drugs will decrease exposure to apixaban [see Clinical Pharmacology (12.3)] .

Apixaban is a substrate of both CYP3A4 and P-gp. Concomitant use with drugs that are combined P-gp and strong CYP3A4 inducers decreases exposure to apixaban [see Clinical Pharmacology (12.3)] which increases the risk for stroke and other thromboembolic events.

7.3 Anticoagulants and Antiplatelet Agents

Coadministration of antiplatelet agents, fibrinolytics, heparin, aspirin, and chronic NSAID use increases the risk of bleeding.

APPRAISE-2, a placebo-controlled clinical trial of ELIQUIS in high-risk, post-acute coronary syndrome patients treated with aspirin or the combination of aspirin and clopidogrel, was terminated early due to a higher rate of bleeding with ELIQUIS compared to placebo. The rate of ISTH major bleeding was 2.8% per year with ELIQUIS versus 0.6% per year with placebo in patients receiving single antiplatelet therapy and was 5.9% per year with ELIQUIS versus 2.5% per year with placebo in those receiving dual antiplatelet therapy.

In ARISTOTLE, concomitant use of aspirin increased the bleeding risk on ELIQUIS from 1.8% per year to 3.4% per year and concomitant use of aspirin and warfarin increased the bleeding risk from 2.7% per year to 4.6% per year. In this clinical trial, there was limited (2.3%) use of dual antiplatelet therapy with ELIQUIS.

8 USE IN SPECIFIC POPULATIONS

8.1 Pregnancy

Risk Summary

The limited available data on ELIQUIS use in pregnant women are insufficient to inform drug-associated risks of major birth defects, miscarriage, or adverse developmental outcomes. Treatment may increase the risk of bleeding during pregnancy and delivery. In animal reproduction studies, no adverse developmental effects were seen when apixaban was administered to rats (orally), rabbits (intravenously) and mice (orally) during organogenesis at unbound apixaban exposure levels up to 4, 1 and 19 times, respectively, the human exposure based on area under plasma-concentration time curve (AUC) at the Maximum Recommended Human Dose (MRHD) of 5 mg twice daily.

The estimated background risk of major birth defects and miscarriage for the indicated populations is unknown. All pregnancies have a background risk of birth defect, loss, or other adverse outcomes. In the U.S. general population, the estimated background risk of major birth defects and miscarriage in clinically recognized pregnancies is 2% to 4% and 15% to 20%, respectively.

Clinical Considerations

Disease-associated maternal and/or embryo/fetal risk

Pregnancy confers an increased risk of thromboembolism that is higher for women with underlying thromboembolic disease and certain high-risk pregnancy conditions. Published data describe that women with a previous history of venous thrombosis are at high risk for recurrence during pregnancy.

Fetal/Neonatal adverse reactions

Use of anticoagulants, including ELIQUIS, may increase the risk of bleeding in the fetus and neonate.

Labor or delivery

All patients receiving anticoagulants, including pregnant women, are at risk for bleeding. ELIQUIS use during labor or delivery in women who are receiving neuraxial anesthesia may result in epidural or spinal hematomas. Consider use of a shorter acting anticoagulant as delivery approaches [see Warnings and Precautions (5.3)] .

Data

Animal Data

No developmental toxicities were observed when apixaban was administered during organogenesis to rats (orally), rabbits (intravenously) and mice (orally) at unbound apixaban exposure levels 4, 1, and 19 times, respectively, the human exposures at the MRHD. There was no evidence of fetal bleeding, although conceptus exposure was confirmed in rats and rabbits. Oral administration of apixaban to rat dams from gestation day 6 through lactation day 21 at maternal unbound apixaban exposures ranging from 1.4 to 5 times the human exposures at the MRHD was not associated with reduced maternal mortality or reduced conceptus/neonatal viability, although increased incidences of peri-vaginal bleeding were observed in dams at all doses. There was no evidence of neonatal bleeding.

8.2 Lactation

Risk Summary

There are no data on the presence of apixaban or its metabolites in human milk, the effects on the breastfed child, or the effects on milk production. Apixaban and/or its metabolites were present in the milk of rats (see Data). Because human exposure through milk is unknown, breastfeeding is not recommended during treatment with ELIQUIS.

Data

Animal Data

Maximal plasma concentrations were observed after 30 minutes following a single oral administration of a 5 mg dose to lactating rats. Maximal milk concentrations were observed 6 hours after dosing. The milk to plasma AUC (0-24) ratio is 30:1 indicating that apixaban can accumulate in milk. The concentrations of apixaban in animal milk does not necessarily predict the concentration of drug in human milk.

8.3 Females and Males of Reproductive Potential

Females of reproductive potential requiring anticoagulation should discuss pregnancy planning with their physician.

The risk of clinically significant uterine bleeding, potentially requiring gynecological surgical interventions, identified with oral anticoagulants including ELIQUIS should be assessed in females of reproductive potential and those with abnormal uterine bleeding.

8.4 Pediatric Use

The safety and effectiveness of ELIQUIS for the treatment of VTE and the reduction in the risk of recurrent VTE have been established in pediatric patients aged birth and older. Use of ELIQUIS for this indication is supported by evidence from adequate and well-controlled studies in adults with additional pharmacokinetic, safety, and efficacy data in pediatric patients. These studies included a randomized, active controlled, open label, multi-center study of ELIQUIS [see Adverse Reactions (6.1)and Clinical Studies (14.4)] .

8.5 Geriatric Use

Of the total subjects in the ARISTOTLE and AVERROES clinical studies, >69% were 65 years of age and older, and >31% were 75 years of age and older. In the ADVANCE-1, ADVANCE-2, and ADVANCE-3 clinical studies, 50% of subjects were 65 years of age and older, while 16% were 75 years of age and older. In the AMPLIFY and AMPLIFY-EXT clinical studies, >32% of subjects were 65 years of age and older and >13% were 75 years of age and older. No clinically significant differences in safety or effectiveness were observed when comparing subjects in different age groups.

8.6 Renal Impairment

Reduction of Risk of Stroke and Systemic Embolism in Patients with Nonvalvular Atrial Fibrillation

The recommended dose is 2.5 mg twice daily in patients with at least two of the following characteristics [see Dosage and Administration (2.1)] :

- age greater than or equal to 80 years
- body weight less than or equal to 60 kg
- serum creatinine greater than or equal to 1.5 mg/dL

Patients with End-Stage Renal Disease on Dialysis

Clinical efficacy and safety studies with ELIQUIS did not enroll patients with end-stage renal disease (ESRD) on dialysis. In patients with ESRD maintained on intermittent hemodialysis, administration of ELIQUIS at the usually recommended dose [see Dosage and Administration (2.1)] will result in concentrations of apixaban and pharmacodynamic activity similar to those observed in the ARISTOTLE study [see Clinical Pharmacology (12.3)] . It is not known whether these concentrations will lead to similar stroke reduction and bleeding risk in patients with ESRD on dialysis as was seen in ARISTOTLE.

Prophylaxis of Deep Vein Thrombosis Following Hip or Knee Replacement Surgery, and Treatment of DVT and PE and Reduction in the Risk of Recurrence of DVT and PE

No dose adjustment is recommended for patients with renal impairment, including those with ESRD on dialysis [see Dosage and Administration (2.1)] . Clinical efficacy and safety studies with ELIQUIS did not enroll patients with ESRD on dialysis or patients with a CrCl <15 mL/min; therefore, dosing recommendations are based on pharmacokinetic and pharmacodynamic (anti-FXa activity) data in subjects with ESRD maintained on dialysis [see Clinical Pharmacology (12.3)].

Treatment of Venous Thromboembolism (VTE) and Reduction in the Risk of Recurrent VTE in Pediatric Patients

In pediatric patients equal to or greater than 2 years of age, ELIQUIS is not recommended in patients with an estimated glomerular filtration rate (eGFR) <30 mL/min/1.73 m^2body surface area (BSA).

In patients less than 2 years of age, ELIQUIS is not recommended in patients with inadequate renal function defined by sex and postnatal age as used in the pediatric VTE trial for ELIQUIS (see Table 12 below).

To estimate GFR, the pediatric VTE trial for ELIQUIS used the updated Schwartz formula, eGFR (ml/min/1.73m^2) = 0.413 * height (cm)/serum creatinine (mg/dL) for serum creatinine measured by an enzymatic creatinine method calibrated to be traceable to isotope dilution mass spectrometry (IDMS).

Table 12: Inadequate renal function by sex and post-natal age in pediatric patients <2 years of age as defined in the pediatric VTE trial for ELIQUIS
Postnatal age (gender) | Threshold eGFR used to define inadequate renal function (mL/min/1.73 m^2)
1 week (males and females) | <8
2–8 weeks (males and females) | <12
>8 weeks to <2 years (males and females) | <22
Inadequate renal function was defined as <30% of 1 standard deviation (SD) below normal GFR for age and size as
determined by the updated Schwartz formula for ages up to 2 years. Beyond 2 years of age, the qualifying GFR for
the pediatric VTE study was ≥30 mL/min/1.73m^2.

8.7 Hepatic Impairment

No dose adjustment is required in patients with mild hepatic impairment (Child-Pugh class A).

Because patients with moderate hepatic impairment (Child-Pugh class B) may have intrinsic coagulation abnormalities and there is limited clinical experience with ELIQUIS in these patients, dosing recommendations cannot be provided [see Clinical Pharmacology (12.2)] .

ELIQUIS is not recommended in patients with severe hepatic impairment (Child-Pugh class C) [see Clinical Pharmacology (12.2)] .

ELIQUIS has not been studied in pediatric patients with hepatic impairment.

10 OVERDOSAGE

Overdose of ELIQUIS increases the risk of bleeding [see Warnings and Precautions (5.2)] .

In healthy subjects, administration of activated charcoal 2 and 6 hours after ingestion of a 20-mg dose of apixaban reduced mean apixaban AUC by 50% and 27%, respectively. Thus, administration of activated charcoal may be useful in the management of ELIQUIS overdose or accidental ingestion. An agent to reverse the anti-factor Xa activity of apixaban is available.

Consider contacting the Poison Help line (1-800-222-1222) or a medical toxicologist for additional overdose management recommendations.

11 DESCRIPTION

ELIQUIS (apixaban), a factor Xa (FXa) inhibitor, is chemically described as 1-(4-methoxyphenyl)-7-oxo-6-[4-(2-oxopiperidin-1-yl)phenyl]-4,5,6,7-tetrahydro-1 H-pyrazolo[3,4- c]pyridine-3-carboxamide. Its molecular formula is C25H25N5O4, which corresponds to a molecular weight of 459.5. Apixaban has the following structural formula:

Apixaban is a white to pale-yellow powder. At physiological pH (1.2-6.8), apixaban does not ionize; its aqueous solubility across the physiological pH range is ~0.04 mg/mL.

ELIQUIS tablets 2.5 mg and 5 mg are available for oral administration and contain the following inactive ingredients: anhydrous lactose, microcrystalline cellulose, croscarmellose sodium, sodium lauryl sulfate, and magnesium stearate. The film coating contains lactose monohydrate, hypromellose, titanium dioxide, triacetin, and yellow iron oxide (2.5 mg tablets) or red iron oxide (5 mg tablets).

ELIQUIS 0.5 mg film coated tablets for oral suspension are supplied in packets containing 1 (0.5 mg), 3 (1.5 mg) or 4 (2 mg) apixaban tablets. The inactive ingredients are anhydrous lactose, microcrystalline cellulose, croscarmellose sodium, sodium lauryl sulfate, and magnesium stearate. The film coating contains lactose monohydrate, hypromellose, titanium dioxide, triacetin, and red iron oxide.

ELIQUIS SPRINKLE 0.15 mg for oral suspension is supplied as a white to off-white powder in capsules, which contain 0.15 mg apixaban and the following inactive ingredients: hypromellose and sugar spheres.

12 CLINICAL PHARMACOLOGY

12.1 Mechanism of Action

Apixaban is a selective inhibitor of FXa. It does not require antithrombin III for antithrombotic activity. Apixaban inhibits free and clot-bound FXa, and prothrombinase activity. Apixaban has no direct effect on platelet aggregation, but indirectly inhibits platelet aggregation induced by thrombin. By inhibiting FXa, apixaban decreases thrombin generation and thrombus development.

12.2 Pharmacodynamics

As a result of FXa inhibition, apixaban prolongs clotting tests such as prothrombin time (PT), INR, and activated partial thromboplastin time (aPTT). Changes observed in these clotting tests at the expected therapeutic dose, however, are small, subject to a high degree of variability, and not useful in monitoring the anticoagulation effect of apixaban.

The Rotachrom®Heparin chromogenic assay was used to measure the effect of apixaban on FXa activity in humans primarily during the apixaban adult development program. A concentration-dependent increase in anti-FXa activity was observed in the dose range tested and was similar in healthy subjects and patients with AF.

This test is not recommended for assessing the anticoagulant effect of apixaban.

Effect of PCCs on Pharmacodynamics of ELIQUIS

There is no clinical experience to reverse bleeding with the use of 4-factor PCC products in individuals who have received ELIQUIS.

Effects of 4-factor PCCs on the pharmacodynamics of apixaban were studied in healthy subjects. Following administration of apixaban dosed to steady state, endogenous thrombin potential (ETP) returned to pre-apixaban levels 4 hours after the initiation of a 30-minute PCC infusion, compared to 45 hours with placebo. Mean ETP levels continued to increase and exceeded pre-apixaban levels reaching a maximum (34%-51% increase over pre-apixaban levels) at 21 hours after initiating PCC and remained elevated (21%-27% increase) at the end of the study (69 hours after initiation of PCC). The clinical relevance of this increase in ETP is unknown.

Pharmacodynamic drug interaction studies with aspirin, clopidogrel, aspirin and clopidogrel, prasugrel, enoxaparin, and naproxen were conducted. No pharmacodynamic interactions were observed with aspirin, clopidogrel, or prasugrel [see Warnings and Precautions (5.2)] . A 50% to 60% increase in anti-FXa activity was observed when ELIQUIS was coadministered with enoxaparin or naproxen.

Specific Populations

Renal impairment:Anti-FXa activity adjusted for exposure to apixaban was similar across renal function categories.

Hepatic impairment:Changes in anti-FXa activity were similar in patients with mild-to-moderate hepatic impairment and healthy subjects. However, in patients with moderate hepatic impairment, there is no clear understanding of the impact of this degree of hepatic function impairment on the coagulation cascade and its relationship to efficacy and bleeding. Patients with severe hepatic impairment were not studied.

Pediatric patients:In pediatric patients treated with apixaban, the correlation between anti-FXa activity and plasma concentration is linear with a slope close to 1.

Cardiac Electrophysiology

Apixaban has no effect on the QTc interval in humans at doses up to 50 mg.

12.3 Pharmacokinetics

Apixaban demonstrates linear pharmacokinetics with dose-proportional increases in exposure for oral doses up to 10 mg.

Absorption

The absolute bioavailability of apixaban is approximately 50% for doses up to 10 mg of ELIQUIS. Food does not affect the bioavailability of apixaban. Maximum concentrations (Cmax) of apixaban appear 3 to 4 hours after oral administration of ELIQUIS. At doses ≥25 mg, apixaban displays dissolution-limited absorption with decreased bioavailability. Following oral administration of 10 mg of apixaban as 2 crushed 5 mg tablets suspended in 30 mL of water, exposure was similar to that after oral administration of 2 intact 5 mg tablets. Following oral administration of 10 mg of apixaban as 2 crushed 5 mg tablets mixed with 30 g of applesauce, the Cmaxand AUC were 20% and 16% lower, respectively, when compared to administration of 2 intact 5 mg tablets. Following administration of a crushed 5 mg ELIQUIS tablet that was suspended in 60 mL D5W and delivered through a nasogastric tube, exposure was similar to that seen in other clinical trials involving healthy volunteers receiving a single oral 5 mg tablet dose.

Distribution

Plasma protein binding in humans is approximately 87%. The volume of distribution (Vss) is approximately 21 liters.

Metabolism

Approximately 25% of an orally administered apixaban dose is recovered in urine and feces as metabolites. Apixaban is metabolized mainly via CYP3A4 with minor contributions from CYP1A2, 2C8, 2C9, 2C19, and 2J2. O-demethylation and hydroxylation at the 3-oxopiperidinyl moiety are the major sites of biotransformation.

Unchanged apixaban is the major drug-related component in human plasma; there are no active circulating metabolites.

Elimination

Apixaban is eliminated in both urine and feces. Renal excretion accounts for about 27% of total clearance. Biliary and direct intestinal excretion contributes to elimination of apixaban in the feces.

Apixaban has a total clearance of approximately 3.3 L/hour and an apparent half-life of approximately 12 hours following oral administration.

Apixaban is a substrate of transport proteins: P-gp and breast cancer resistance protein.

Drug Interaction Studies

In in vitroapixaban studies at concentrations significantly greater than therapeutic exposures, no inhibitory effect on the activity of CYP1A2, CYP2A6, CYP2B6, CYP2C8, CYP2C9, CYP2D6, CYP3A4/5, or CYP2C19, nor induction effect on the activity of CYP1A2, CYP2B6, or CYP3A4/5 were observed. Therefore, apixaban is not expected to alter the metabolic clearance of coadministered drugs that are metabolized by these enzymes. Apixaban is not a significant inhibitor of P-gp.

The effects of coadministered drugs on the pharmacokinetics of apixaban are summarized in Figure 2 [see also Warnings and Precautions (5.2)and Drug Interactions (7)] .

Figure 2: Effect of Coadministered Drugs on the Pharmacokinetics of Apixaban

In dedicated studies conducted in healthy subjects, famotidine, atenolol, prasugrel, and enoxaparin did not meaningfully alter the pharmacokinetics of apixaban.

In studies conducted in healthy subjects, apixaban did not meaningfully alter the pharmacokinetics of digoxin, naproxen, atenolol, prasugrel, or acetylsalicylic acid.

Specific Populations

The effects of level of renal impairment, age, body weight, and level of hepatic impairment on the pharmacokinetics of apixaban are summarized in Figure 3.

Figure 3: Effect of Specific Populations on the Pharmacokinetics of Apixaban

* ESRD subjects treated with intermittent hemodialysis; reported PK findings are following single dose of apixaban posthemodialysis.
† Results reflect CrCl of 15 mL/min based on regression analysis.
‡ Dashed vertical lines illustrate pharmacokinetic changes that were used to inform dosing recommendations.
§ No dose adjustment is recommended for nonvalvular atrial fibrillation patients unless at least 2 of the following patient characteristics (age greater than or equal to 80 years, body weight less than or equal to 60 kg, or serum creatinine greater than or equal to 1.5 mg/dL) are present.

Gender:A study in healthy subjects comparing the pharmacokinetics in males and females showed no meaningful difference.

Race:The results across pharmacokinetic studies in normal subjects showed no differences in apixaban pharmacokinetics among White/Caucasian, Asian, and Black/African American subjects. No dose adjustment is required based on race/ethnicity.

Hemodialysis in ESRD subjects:Systemic exposure to apixaban administered as a single 5 mg dose in ESRD subjects dosed immediately after the completion of a 4-hour hemodialysis session (postdialysis) is 36% higher when compared to subjects with normal renal function (Figure 3). The systemic exposure to apixaban administered 2 hours prior to a 4-hour hemodialysis session with a dialysate flow rate of 500 mL/min and a blood flow rate in the range of 350 to 500 mL/min is 17% higher compared to those with normal renal function. The dialysis clearance of apixaban is approximately 18 mL/min. The systemic exposure of apixaban is 14% lower on dialysis when compared to not on dialysis.

Protein binding was similar (92%-94%) between healthy controls and ESRD subjects during the on-dialysis and off-dialysis periods.

Pediatric Patients:Apixaban reached maximum concentration (Cmax) in pediatric patients approximately 2 hours after single-dose administration. In pediatric patients, apixaban has a total apparent clearance of about 3.0 L/h.

An exploratory analysis in pediatric patients did not reveal relevant differences in apixaban exposure based on gender or race.

13 NONCLINICAL TOXICOLOGY

13.1 Carcinogenesis, Mutagenesis, Impairment of Fertility

Carcinogenesis:Apixaban was not carcinogenic when administered to mice and rats for up to 2 years. The systemic exposures (AUCs) of unbound apixaban in male and female mice at the highest doses tested (1500 and 3000 mg/kg/day) were 9 and 20 times, respectively, the human exposure of unbound drug at the MRHD of 10 mg/day. Systemic exposures of unbound apixaban in male and female rats at the highest dose tested (600 mg/kg/day) were 2 and 4 times, respectively, the human exposure.

Mutagenesis:Apixaban was neither mutagenic in the bacterial reverse mutation (Ames) assay, nor clastogenic in Chinese hamster ovary cells in vitro, in a 1-month in vivo/in vitrocytogenetics study in rat peripheral blood lymphocytes, or in a rat micronucleus study in vivo.

Impairment of Fertility:Apixaban had no effect on fertility in male or female rats when given at doses up to 600 mg/kg/day, a dose resulting in unbound apixaban exposure levels that are 3 and 4 times, respectively, the human exposure.

Apixaban administered to female rats at doses up to 1000 mg/kg/day from implantation through the end of lactation produced no adverse findings in male offspring (F1 generation) at doses up to 1000 mg/kg/day, a dose resulting in exposure to unbound apixaban that is 5 times the human exposure. Adverse effects in the F1-generation female offspring were limited to decreased mating and fertility indices at ≥200 mg/kg/day (a dose resulting in exposure to unbound apixaban that is ≥5 times the human exposure).

14 CLINICAL STUDIES

14.1 Reduction of Risk of Stroke and Systemic Embolism in Nonvalvular Atrial Fibrillation

ARISTOTLE

Evidence for the efficacy and safety of ELIQUIS was derived from ARISTOTLE, a multinational, double-blind study in patients with nonvalvular AF comparing the effects of ELIQUIS and warfarin on the risk of stroke and non-central nervous system (CNS) systemic embolism. In ARISTOTLE, patients were randomized to ELIQUIS 5 mg orally twice daily (or 2.5 mg twice daily in subjects with at least 2 of the following characteristics: age greater than or equal to 80 years, body weight less than or equal to 60 kg, or serum creatinine greater than or equal to 1.5 mg/dL) or to warfarin (targeted to an INR range of 2.0-3.0). Patients had to have one or more of the following additional risk factors for stroke:

- prior stroke or transient ischemic attack (TIA)
- prior systemic embolism
- age greater than or equal to 75 years
- arterial hypertension requiring treatment
- diabetes mellitus
- heart failure ≥New York Heart Association Class 2
- left ventricular ejection fraction ≤40%

The primary objective of ARISTOTLE was to determine whether ELIQUIS 5 mg twice daily (or 2.5 mg twice daily) was effective (noninferior to warfarin) in reducing the risk of stroke (ischemic or hemorrhagic) and systemic embolism. Superiority of ELIQUIS to warfarin was also examined for the primary endpoint (rate of stroke and systemic embolism), major bleeding, and death from any cause.

A total of 18,201 patients were randomized and followed on study treatment for a median of 89 weeks. Forty-three percent of patients were vitamin K antagonist (VKA) “naive,” defined as having received ≤30 consecutive days of treatment with warfarin or another VKA before entering the study. The mean age was 69 years and the mean CHADS2score (a scale from 0 to 6 used to estimate risk of stroke, with higher scores predicting greater risk) was 2.1. The population was 65% male, 83% Caucasian, 14% Asian, and 1% Black. There was a history of stroke, TIA, or non-CNS systemic embolism in 19% of patients. Concomitant diseases of patients in this study included hypertension 88%, diabetes 25%, congestive heart failure (or left ventricular ejection fraction ≤40%) 35%, and prior myocardial infarction 14%. Patients treated with warfarin in ARISTOTLE had a mean percentage of time in therapeutic range (INR 2.0-3.0) of 62%.

ELIQUIS was superior to warfarin for the primary endpoint of reducing the risk of stroke and systemic embolism (Table 13 and Figure 4). Superiority to warfarin was primarily attributable to a reduction in hemorrhagic stroke and ischemic strokes with hemorrhagic conversion compared to warfarin. Purely ischemic strokes occurred with similar rates on both drugs.

ELIQUIS also showed significantly fewer major bleeds than warfarin [see Adverse Reactions (6.1)] .

Table 13: Key Efficacy Outcomes in Patients with Nonvalvular Atrial Fibrillation in ARISTOTLE (Intent-to-Treat Analysis)
 | ELIQUIS N=9120 n (%/year) | Warfarin N=9081 n (%/year) | Hazard Ratio (95% CI) | P-value
Stroke or systemic embolism | 212 (1.27) | 265 (1.60) | 0.79 (0.66, 0.95) | 0.01
Stroke | 199 (1.19) | 250 (1.51) | 0.79 (0.65, 0.95)
Ischemic without hemorrhage | 140 (0.83) | 136 (0.82) | 1.02 (0.81, 1.29)
Ischemic with hemorrhagic conversion | 12 (0.07) | 20 (0.12) | 0.60 (0.29, 1.23)
Hemorrhagic | 40 (0.24) | 78 (0.47) | 0.51 (0.35, 0.75)
Unknown | 14 (0.08) | 21 (0.13) | 0.65 (0.33, 1.29)
Systemic embolism | 15 (0.09) | 17 (0.10) | 0.87 (0.44, 1.75)
The primary endpoint was based on the time to first event (one per subject). Component counts are for subjects with any event, not necessarily the first.

Figure 4: Kaplan-Meier Estimate of Time to First Stroke or Systemic Embolism in ARISTOTLE (Intent-to-Treat Population)

All-cause death was assessed using a sequential testing strategy that allowed testing for superiority if effects on earlier endpoints (stroke plus systemic embolus and major bleeding) were demonstrated. ELIQUIS treatment resulted in a significantly lower rate of all-cause death (p = 0.046) than did treatment with warfarin, primarily because of a reduction in cardiovascular death, particularly stroke deaths. Non-vascular death rates were similar in the treatment arms.

In ARISTOTLE, the results for the primary efficacy endpoint were generally consistent across most major subgroups including weight, CHADS2score (a scale from 0 to 6 used to predict risk of stroke in patients with AF, with higher scores predicting greater risk), prior warfarin use, level of renal impairment, geographic region, and aspirin use at randomization (Figure 5).

Figure 5: Stroke and Systemic Embolism Hazard Ratios by Baseline Characteristics – ARISTOTLE Study

Note: The figure above presents effects in various subgroups, all of which are baseline characteristics and all of which were prespecified, if not the groupings. The 95% confidence limits that are shown do not take into account how many comparisons were made, nor do they reflect the effect of a particular factor after adjustment for all other factors. Apparent homogeneity or heterogeneity among groups should not be over-interpreted.

At the end of the ARISTOTLE study, warfarin patients who completed the study were generally maintained on a VKA with no interruption of anticoagulation. ELIQUIS patients who completed the study were generally switched to a VKA with a 2-day period of coadministration of ELIQUIS and VKA, so that some patients may not have been adequately anticoagulated after stopping ELIQUIS until attaining a stable and therapeutic INR. During the 30 days following the end of the study, there were 21 stroke or systemic embolism events in the 6791 patients (0.3%) in the ELIQUIS arm compared to 5 in the 6569 patients (0.1%) in the warfarin arm [see Dosage and Administration (2.4)] .

AVERROES

In AVERROES, patients with nonvalvular atrial fibrillation thought not to be candidates for warfarin therapy were randomized to treatment with ELIQUIS 5 mg orally twice daily (or 2.5 mg twice daily in selected patients) or aspirin 81 to 324 mg once daily. The primary objective of the study was to determine if ELIQUIS was superior to aspirin for preventing the composite outcome of stroke or systemic embolism. AVERROES was stopped early on the basis of a prespecified interim analysis showing a significant reduction in stroke and systemic embolism for ELIQUIS compared to aspirin that was associated with a modest increase in major bleeding (Table 14) [see Adverse Reactions (6.1)] .

Table 14: Key Efficacy Outcomes in Patients with Nonvalvular Atrial Fibrillation in AVERROES
 | ELIQUIS N=2807 n (%/year) | Aspirin N=2791 n (%/year) | Hazard Ratio (95% CI) | P-value
Stroke or systemic embolism | 51 (1.62) | 113 (3.63) | 0.45 (0.32, 0.62) | <0.0001
Stroke
Ischemic or undetermined | 43 (1.37) | 97 (3.11) | 0.44 (0.31, 0.63) | -
Hemorrhagic | 6 (0.19) | 9 (0.28) | 0.67 (0.24, 1.88) | -
Systemic embolism | 2 (0.06) | 13 (0.41) | 0.15 (0.03, 0.68) | -
MI | 24 (0.76) | 28 (0.89) | 0.86 (0.50, 1.48) | -
All-cause death | 111 (3.51) | 140 (4.42) | 0.79 (0.62, 1.02) | 0.068
Vascular death | 84 (2.65) | 96 (3.03) | 0.87 (0.65, 1.17) | -

14.2 Prophylaxis of Deep Vein Thrombosis Following Hip or Knee Replacement Surgery

The clinical evidence for the effectiveness of ELIQUIS is derived from the ADVANCE-1, ADVANCE-2, and ADVANCE-3 clinical trials in adult patients undergoing elective hip (ADVANCE-3) or knee (ADVANCE-2 and ADVANCE-1) replacement surgery. A total of 11,659 patients were randomized in 3 double-blind, multi-national studies. Included in this total were 1866 patients age 75 or older, 1161 patients with low body weight (≤60 kg), 2528 patients with Body Mass Index ≥33 kg/m^2, and 625 patients with severe or moderate renal impairment.

In the ADVANCE-3 study, 5407 patients undergoing elective hip replacement surgery were randomized to receive either ELIQUIS 2.5 mg orally twice daily or enoxaparin 40 mg subcutaneously once daily. The first dose of ELIQUIS was given 12 to 24 hours post surgery, whereas enoxaparin was started 9 to 15 hours prior to surgery. Treatment duration was 32 to 38 days.

In patients undergoing elective knee replacement surgery, ELIQUIS 2.5 mg orally twice daily was compared to enoxaparin 40 mg subcutaneously once daily (ADVANCE-2, N=3057) or enoxaparin 30 mg subcutaneously every 12 hours (ADVANCE-1, N=3195). In the ADVANCE-2 study, the first dose of ELIQUIS was given 12 to 24 hours postsurgery, whereas enoxaparin was started 9 to 15 hours prior to surgery. In the ADVANCE-1 study, both ELIQUIS and enoxaparin were initiated 12 to 24 hours post surgery. Treatment duration in both ADVANCE-2 and ADVANCE-1 was 10 to 14 days.

In all 3 studies, the primary endpoint was a composite of adjudicated asymptomatic and symptomatic DVT, nonfatal PE, and all-cause death at the end of the double-blind intended treatment period. In ADVANCE-3 and ADVANCE-2, the primary endpoint was tested for noninferiority, then superiority, of ELIQUIS to enoxaparin. In ADVANCE-1, the primary endpoint was tested for noninferiority of ELIQUIS to enoxaparin.

The efficacy data are provided in Tables 15 and 16.

Table 15: Summary of Key Efficacy Analysis Results During the Intended Treatment Period for Patients Undergoing Elective Hip Replacement Surgery*
 | ADVANCE-3
Events During 35-Day Treatment Period | ELIQUIS 2.5 mg po bid | Enoxaparin 40 mg sc qd | Relative Risk (95% CI) P-value
Number of Patients | N=1949 | N=1917
Total VTE†/All-cause death | 27 (1.39%) (0.95, 2.02) | 74 (3.86%) (3.08, 4.83) | 0.36 (0.22, 0.54) p<0.0001
Number of Patients | N=2708 | N=2699
All-cause death | 3 (0.11%) (0.02, 0.35) | 1 (0.04%) (0.00, 0.24)
PE | 3 (0.11%) (0.02, 0.35) | 5 (0.19%) (0.07, 0.45)
Symptomatic DVT | 1 (0.04%) (0.00, 0.24) | 5 (0.19%) (0.07, 0.45)
Number of Patients | N=2196 | N=2190
Proximal DVT‡ | 7 (0.32%) (0.14, 0.68) | 20 (0.91%) (0.59, 1.42)
Number of Patients | N=1951 | N=1908
Distal DVT‡ | 20 (1.03%) (0.66, 1.59) | 57 (2.99%) (2.31, 3.86)
* Events associated with each endpoint were counted once per subject but subjects may have contributed events to multiple endpoints.
† Total VTE includes symptomatic and asymptomatic DVT and PE.
‡ Includes symptomatic and asymptomatic DVT.

Table 16: Summary of Key Efficacy Analysis Results During the Intended Treatment Period for Patients Undergoing Elective Knee Replacement Surgery*
 | ADVANCE-1 |  |  | ADVANCE-2
Events during 12-day treatment period | ELIQUIS 2.5 mg po bid | Enoxaparin 30 mg sc q12h | Relative Risk (95% CI) P-value | ELIQUIS 2.5 mg po bid | Enoxaparin 40 mg sc; qd | Relative Risk (95% CI); P-value
Number of Patients | N=1157 | N=1130 |  | N=976 | N=997
Total VTE†/All-cause death | 104 (8.99%) (7.47, 10.79) | 100 (8.85%) (7.33, 10.66) | 1.02 (0.78, 1.32) NS | 147 (15.06%) (12.95, 17.46) | 243 (24.37%) (21.81, 27.14) | 0.62 (0.51, 0.74) p<0.0001
Number of Patients | N=1599 | N=1596 |  | N=1528 | N=1529
All-cause death | 3 (0.19%) (0.04, 0.59) | 3 (0.19%) (0.04, 0.59) |  | 2 (0.13%) (0.01, 0.52) | 0 (0%) (0.00, 0.31)
PE | 16 (1.0%) (0.61, 1.64) | 7 (0.44%) (0.20, 0.93) |  | 4 (0.26%) (0.08, 0.70) | 0 (0%) (0.00, 0.31)
Symptomatic DVT | 3 (0.19%) (0.04, 0.59) | 7 (0.44%) (0.20, 0.93) |  | 3 (0.20%) (0.04, 0.61) | 7 (0.46%) (0.20, 0.97)
Number of Patients | N=1254 | N=1207 |  | N=1192 | N=1199
Proximal DVT‡ | 9 (0.72%) (0.36, 1.39) | 11 (0.91%) (0.49, 1.65) |  | 9 (0.76%) (0.38, 1.46) | 26 (2.17%) (1.47, 3.18)
Number of Patients | N=1146 | N=1133 |  | N=978 | N=1000
Distal DVT‡ | 83 (7.24%) (5.88, 8.91) | 91 (8.03%) (6.58, 9.78) |  | 142 (14.52%) (12.45, 16.88) | 239 (23.9%) (21.36, 26.65)
* Events associated with each endpoint were counted once per subject but subjects may have contributed events to multiple endpoints.
† Total VTE includes symptomatic and asymptomatic DVT and PE.
‡ Includes symptomatic and asymptomatic DVT.

The efficacy profile of ELIQUIS was generally consistent across subgroups of interest for this indication (e.g., age, gender, race, body weight, renal impairment).

14.3 Treatment of DVT and PE and Reduction in the Risk of Recurrence of DVT and PE

Efficacy and safety of ELIQUIS for the treatment of DVT and PE, and for the reduction in the risk of recurrent DVT and PE following 6 to 12 months of anticoagulant treatment was derived from the AMPLIFY and AMPLIFY-EXT studies. Both studies were randomized, parallel-group, double-blind trials in patients with symptomatic proximal DVT and/or symptomatic PE. All key safety and efficacy endpoints were adjudicated in a blinded manner by an independent committee.

AMPLIFY

The primary objective of AMPLIFY was to determine whether ELIQUIS was noninferior to enoxaparin/warfarin for the incidence of recurrent VTE (venous thromboembolism) or VTE-related death. Patients with an objectively confirmed symptomatic DVT and/or PE were randomized to treatment with ELIQUIS 10 mg twice daily orally for 7 days followed by ELIQUIS 5 mg twice daily orally for 6 months, or enoxaparin 1 mg/kg twice daily subcutaneously for at least 5 days (until INR ≥2) followed by warfarin (target INR range 2.0-3.0) orally for 6 months. Patients who required thrombectomy, insertion of a caval filter, or use of a fibrinolytic agent, and patients with creatinine clearance <25 mL/min, significant liver disease, an existing heart valve or atrial fibrillation, or active bleeding were excluded from the AMPLIFY study. Patients were allowed to enter the study with or without prior parenteral anticoagulation (up to 48 hours).

A total of 5244 patients were evaluable for efficacy and were followed for a mean of 154 days in the ELIQUIS group and 152 days in the enoxaparin/warfarin group. The mean age was 57 years. The AMPLIFY study population was 59% male, 83% Caucasian, 8% Asian, and 4% Black. For patients randomized to warfarin, the mean percentage of time in therapeutic range (INR 2.0-3.0) was 60.9%.

Approximately 90% of patients enrolled in AMPLIFY had an unprovoked DVT or PE at baseline. The remaining 10% of patients with a provoked DVT or PE were required to have an additional ongoing risk factor in order to be randomized, which included previous episode of DVT or PE, immobilization, history of cancer, active cancer, and known prothrombotic genotype.

ELIQUIS was shown to be noninferior to enoxaparin/warfarin in the AMPLIFY study for the primary endpoint of recurrent symptomatic VTE (nonfatal DVT or nonfatal PE) or VTE-related death over 6 months of therapy (Table 17).

Table 17: Efficacy Results in the AMPLIFY Study
 | ELIQUIS N=2609 n | Enoxaparin/Warfarin N=2635 n | Relative Risk (95% CI)
VTE or VTE-related death* | 59 (2.3%) | 71 (2.7%) | 0.84 (0.60, 1.18)
DVT† | 22 (0.8%) | 35 (1.3%)
PE† | 27 (1.0%) | 25 (0.9%)
VTE-related death† | 12 (0.4%) | 16 (0.6%)
VTE or all-cause death | 84 (3.2%) | 104 (4.0%) | 0.82 (0.61, 1.08)
VTE or CV-related death | 61 (2.3%) | 77 (2.9%) | 0.80 (0.57, 1.11)
* Noninferior compared to enoxaparin/warfarin (P-value <0.0001).
† Events associated with each endpoint were counted once per subject, but subjects may have contributed events to multiple endpoints.

In the AMPLIFY study, patients were stratified according to their index event of PE (with or without DVT) or DVT (without PE). Efficacy in the initial treatment of VTE was consistent between the two subgroups.

AMPLIFY-EXT

Patients who had been treated for DVT and/or PE for 6 to 12 months with anticoagulant therapy without having a recurrent event were randomized to treatment with ELIQUIS 2.5 mg orally twice daily, ELIQUIS 5 mg orally twice daily, or placebo for 12 months. Approximately one-third of patients participated in the AMPLIFY study prior to enrollment in the AMPLIFY-EXT study.

A total of 2482 patients were randomized to study treatment and were followed for a mean of approximately 330 days in the ELIQUIS group and 312 days in the placebo group. The mean age in the AMPLIFY-EXT study was 57 years. The study population was 57% male, 85% Caucasian, 5% Asian, and 3% Black.

The AMPLIFY-EXT study enrolled patients with either an unprovoked DVT or PE at baseline (approximately 92%) or patients with a provoked baseline event and one additional risk factor for recurrence (approximately 8%). However, patients who had experienced multiple episodes of unprovoked DVT or PE were excluded from the AMPLIFY-EXT study. In the AMPLIFY-EXT study, both doses of ELIQUIS were superior to placebo in the primary endpoint of symptomatic, recurrent VTE (nonfatal DVT or nonfatal PE), or all-cause death (Table 18).

Table 18: Efficacy Results in the AMPLIFY-EXT Study
 |  |  |  | Relative Risk (95% CI)
 | ELIQUIS 2.5 mg bid N=840 | ELIQUIS 5 mg bid N=813 | Placebo N=829 | ELIQUIS 2.5 mg bid vs Placebo | ELIQUIS 5 mg bid vs Placebo
 | n (%)
Recurrent VTE or all-cause death | 32 (3.8) | 34 (4.2) | 96 (11.6) | 0.33 (0.22, 0.48) p<0.0001 | 0.36 (0.25, 0.53) p<0.0001
DVT* | 19 (2.3) | 28 (3.4) | 72 (8.7)
PE* | 23 (2.7) | 25 (3.1) | 37 (4.5)
All-cause death | 22 (2.6) | 25 (3.1) | 33 (4.0)

* Patients with more than one event are counted in multiple rows.

14.4 Treatment of VTE and Prevention of Recurrent VTE in Pediatric Patients from birth and older

Study CV185325

ELIQUIS for the treatment of venous thromboembolism (VTE) and reduction in the risk of recurrent VTE was evaluated in Study CV185325, a multicenter, randomized, active-controlled, open-label, multi-center study in 229 pediatric patients from birth to less than 18 years with confirmed VTE. This was a descriptive study and no formal inferences were performed. There were 137 patients aged 12 to < 18 years, 44 patients aged 2 to < 12 years, 32 patients aged 28 days to less than 2 years and 16 patients from birth to less than 27 days. Overall, the median age was 14.2 years with a range of 0.04 to 18.0 years. Neonates and infants were excluded from enrollment if they were < 34 weeks’ gestation (until age of > 6 months) or had a body weight of < 2.6 kg. For pre-term infants born between 34 and <37 weeks gestation, neonates who reached 37 weeks starting from actual date of birth (postnatal age), from 27 day neonatal period starting from actual date of birth (postnatal age), or from when the postmenstrual age (gestational age defined as time elapsed between first day of last normal menstrual period and the day of delivery plus postnatal age) and enrolled the neonate no more than 27 days thereafter. There were 101 (44.1%) males, and 128 (55.9%) females in the study. One hundred and seventy-five (76.4%) patients were White, 31 (13.5%) were Black, 9 (3.9%) were Asian, 4 (1.7%) were Other, 2 (0.9%) were Multiracial and 1 (0.4%) was American Indian or Alaska Native, and 7 (3.1%) were missing this information. Twenty-five (10.9%) were Hispanic or Latino and 204 (89.1%) were not Hispanic or Latino.

Index VTE was classified as deep venous thrombosis (DVT), pulmonary embolism (PE), device-related thrombosis (neonatal population only), and other VTE (i.e. cerebral vein and sinus thrombosis, renal vein thrombosis, intracardiac thrombus). Prior to randomization, patients could be treated with SOC anticoagulation for up to 14 days; overall mean (SD) duration of treatment with SOC anticoagulation prior to randomization was 4.9 (2.6) days, and for 92.9% of patients the duration was between 0 and 7 days. Patients were randomized according to a 2:1 ratio to receive either an age-appropriate formulation and body weight-adjusted doses of ELIQUIS or SOC. For patients 2 to less than 18 years, SOC was comprised of low molecular weight heparins (LMWH), unfractionated heparins (UFH) or vitamin K antagonists (VKA). For patients 28 days to less than 2 years of age, SOC was limited to heparins (UFH or LMWH). The main treatment phase lasted 6 to 12 weeks for patients aged birth to less than 2 years, and 12 weeks for patients aged greater than 2 years. Patients aged 28 days to less than 18 years who were randomized to receive apixaban had the option to continue apixaban treatment for 6 to 12 additional weeks in the extension phase.

A diagnostic imaging test was obtained at baseline, at week 6, and end of treatment for patients ≥2 years of age and at baseline and end of treatment for <2 years of age.

Table 19: Primary efficacy results from Study CV185325
 | ELIQUIS N=155 | Standard of care ** N=74
Symptomatic and asymptomatic recurrent VTE* and VTE* related mortality***
Number (%) Subjects with Event | 4 (2.6) | 2 (2.7)
95% Confidence Interval (1) | (0.7, 6.5) | (0.3, 9.4)
* Recurrent VTE, defined as either contiguous progression or non-contiguous new thrombus and including, but not limited to DVT, PE and paradoxical embolism.
(1) 95% Confidence Interval calculated using the Clopper-Pearson exact method
** UFH/LMWH for patients less than 2 years of age and UFH/LMWH/VKA for those equal to or greater than 2 years of age.
*** no VTE related mortality was observed in either treatment arms during the study.

16 HOW SUPPLIED/STORAGE AND HANDLING

HOW SUPPLIED

How Supplied

ELIQUIS (apixaban) tablets for oral use, ELIQUIS (apixaban) tablets for oral suspension

5 mg, Film-coated Tablet,Pink, oval, biconvex, Debossed with “894”on one side and “5” on the other side

NDC: 70518-4462-00

PACKAGING: 30 in 1 BLISTER PACK

Storage and Handling

Store ELIQUIS and ELIQUIS SPRINKLE at 20°C to 25°C (68°F to 77°F); excursions permitted between 15°C to 30°C (59°F to 86°F) [see USP Controlled Room Temperature].

Repackaged and Distributed By:

Remedy Repack, Inc.

625 Kolter Dr. Suite #4 Indiana, PA 1-724-465-8762

STORAGE AND HANDLING

Storage and Handling

Store ELIQUIS and ELIQUIS SPRINKLE at 20°C to 25°C (68°F to 77°F); excursions permitted between 15°C to 30°C (59°F to 86°F) [see USP Controlled Room Temperature].

17 PATIENT COUNSELING INFORMATION

Advise patients to read the FDA-approved patient labeling (Medication Guide and Instructions for Use).

Advise patients of the following:

- Not to discontinue ELIQUIS without talking to their physician first.
- That it might take longer than usual for bleeding to stop, and they may bruise or bleed more easily when treated with ELIQUIS. Advise patients about how to recognize bleeding or symptoms of hypovolemia and of the urgent need to report any unusual bleeding to their physician.
- To tell their physicians and dentists they are taking ELIQUIS, and/or any other product known to affect bleeding (including nonprescription products, such as aspirin or NSAIDs), before any surgery or medical or dental procedure is scheduled and before any new drug is taken.
- If the patient is having neuraxial anesthesia or spinal puncture, inform the patient to watch for signs and symptoms of spinal or epidural hematomas [see Warnings and Precautions (5.3)] . If any of these symptoms occur, advise the patient to seek emergent medical attention.
- To tell their physicians if they are pregnant or plan to become pregnant or are breastfeeding or intend to breastfeed during treatment with ELIQUIS [see Use in Specific Populations (8.1, 8.2)].
- How to take ELIQUIS if they cannot swallow or require a nasogastric tube [see Dosage and Administration (2.7)].
- What to do if a dose is missed [see Dosage and Administration (2.2 and 2.3)].

Pediatric Patients

Advise the caregiver or the patient of the following:

- To always give this medicine exactly as the child’s physician or pharmacist has instructed them.
- The importance of keeping scheduled physician’s visits. ELIQUIS dose is based on body weight and the dose may need to be adjusted as the child’s weight changes. This ensures that the child receives the correct dose of ELIQUIS. The physician may adjust the child’s dose when needed. The caregiver should be advised not to adjust the dose themselves.
- What to do if the child vomits or spits up. If a child vomits or spits up within 30 minutes after taking ELIQUIS, repeat the dose. If a child vomits or spits up more than 30 minutes after taking ELIQUIS, do not repeat the dose. Continue to give the next ELIQUIS dose at the next scheduled time. The caregiver should contact the physician if the child repeatedly vomits or spits up after taking ELIQUIS.

Repackaged By / Distributed By: RemedyRepack Inc.

625 Kolter Drive, Indiana, PA 15701

(724) 465-8762

Repackaged and Distributed By:

Remedy Repack, Inc.

625 Kolter Dr. Suite #4 Indiana, PA 1-724-465-8762

MEDICATION GUIDE

ELIQUIS®(ELL eh kwiss)

(apixaban)

tablets

ELIQUIS®(ELL eh kwiss) SPRINKLE (SPRINK el)

(apixaban)

for oral suspension

What is the most important information I should know about ELIQUIS?

ELIQUIS may cause serious side effects, including:

- Increased risk of blood clots if you stop taking ELIQUIS.
- ELIQUIS lowers your chance of having a stroke by helping to prevent clots from forming. If you stop taking ELIQUIS, you may have increased risk of forming a clot in your blood.
- Do not stop taking ELIQUIS without talking to the healthcare provider who prescribes it for you. Stopping ELIQUIS increases your risk of having a stroke.
- ELIQUIS may need to be stopped, if possible, prior to surgery or a medical or dental procedure. Ask the healthcare provider who prescribed ELIQUIS for you when you should stop taking it. Your healthcare provider will tell you when you may start taking ELIQUIS again after your surgery or procedure. If you have to stop taking ELIQUIS, your healthcare provider may prescribe another medicine to help prevent a blood clot from forming.
- Increased risk of bleeding.ELIQUIS can cause bleeding which can be serious and may lead to death. This is because ELIQUIS is a blood thinner medicine that reduces blood clotting.
- You may have a higher risk of bleeding if you take ELIQUIS and take other medicines that increase your risk of bleeding, including:
- aspirin or aspirin-containing products
- long-term (chronic) use of nonsteroidal anti-inflammatory drugs (NSAIDs)
- warfarin sodium
- any medicine that contains heparin
- clopidogrel
- selective serotonin reuptake inhibitors (SSRIs) or serotonin norepinephrine reuptake inhibitors (SNRIs)
- other medicines to help prevent or treat blood clots
- Tell your healthcare providerif you take any of these medicines. Ask your healthcare provider or pharmacist if you are not sure if your medicine is one listed above.
- During treatment with ELIQUIS:
- you may bruise more easily
- it may take longer than usual for any bleeding to stop
- Call your healthcare provider or get medical help right away if you or your child develop any of these signs or symptoms of bleeding during treatment with ELIQUIS:
- unexpected bleeding or bruising, or bleeding that lasts a long time, such as:
  - unusual bleeding from the gums
  - nosebleeds that happen often
  - menstrual bleeding or vaginal bleeding that is heavier than normal
- bleeding that is severe or you cannot control
- red, pink, or brown urine
- red or black stools (looks like tar)
- cough up blood or blood clots
- vomit blood or your vomit looks like “coffee grounds”
- unexpected pain, swelling, or joint pain
- headaches, feeling dizzy or weak
- Spinal or epidural blood clots (hematoma).People who take a blood thinner medicine (anticoagulant) like ELIQUIS, and have medicine injected into their spinal and epidural area, or have a spinal puncture have a risk of forming a blood clot that can cause long-term or permanent loss of the ability to move (paralysis). Your risk of developing a spinal or epidural blood clot is higher if:
- a thin tube called an epidural catheter is placed in your back to give you certain medicine
- you take NSAIDs or a medicine to prevent blood from clotting
- you have a history of difficult or repeated epidural or spinal punctures
- you have a history of problems with your spine or have had surgery on your spine
- If you take ELIQUIS and receive spinal anesthesia or have a spinal puncture, your healthcare provider should watch you closely for symptoms of spinal or epidural blood clots or bleeding. Tell your healthcare provider or get medical help right away if you have back pain, tingling, numbness, or muscle weakness, especially in your legs and feet, or loss of control of the bowels or bladder (incontinence).
- ELIQUIS is not for use in people with artificial heart valves.
- ELIQUIS is not for use in people with antiphospholipid syndrome (APS), especially with positive triple antibody testing.

What is ELIQUIS?

ELIQUIS is a prescription medicine used in adults to:

- reduce the risk of stroke and blood clots in people who have atrial fibrillation (a type of irregular heartbeat) that is not caused by a heart valve problem.
- help prevent a blood clot in the veins of your legs (deep vein thrombosis or DVT) and lungs (pulmonary embolism or PE) of people who have just had hip or knee replacement surgery.
- treat deep vein thrombosis (DVT) or pulmonary embolism (PE)
- reduce the risk of DVT or PE from happening again after receiving treatment for blood clots.

ELIQUIS is used in children from birth and older to treat blood clots in the veins of your legs and lungs (venous thromboembolism) after at least 5 days of initial anticoagulant treatment, and to reduce the risk of them happening again.

ELIQUIS was not studied and is not recommended in children who weigh less than 5.7 pounds (2.6 kg).

Do not take ELIQUIS if you or your child:

- currently have certain types of abnormal bleeding.
- have had a severe allergic reaction to apixaban or any of the ingredients in ELIQUIS. Ask your healthcare provider if you are not sure. See the end of this Medication Guide for a complete list of ingredients in ELIQUIS.

Before taking ELIQUIS, tell your healthcare provider about all of your medical conditions, including if you or your child:

- have or ever had bleeding problems
- have kidney or liver problems
- have antiphospholipid syndrome (APS)
- are pregnant or plan to become pregnant. It is not known if ELIQUIS will harm your unborn baby.
  - Tell your healthcare providerright away if you become pregnant during treatment with ELIQUIS. Taking ELIQUIS during pregnancy may increase the risk of bleeding in you or in your unborn baby.
  - Females who are able to become pregnant: Talk with your healthcare provider about pregnancy planning during treatment with ELIQUIS. Talk with your healthcare provider about your risk for severe uterine bleeding if you are treated with ELIQUIS.
  - If you take ELIQUIS during pregnancy, tell your healthcare provider right away if you develop any signs or symptoms of bleeding or blood loss. See “What is the most important information I should know about ELIQUIS?” for signs and symptoms of bleeding.
- are breastfeeding or plan to breastfeed. It is not known if ELIQUIS passes into your breast milk. Do not breastfeed during treatment with ELIQUIS. Talk to your healthcare provider about the best way to feed your baby during treatment with ELIQUIS.

Tell all of your healthcare providers and dentists that you or your child are taking ELIQUIS. They should talk to the healthcare provider who prescribed ELIQUIS for you, before you have anysurgery, medical or dental procedure.

Tell your healthcare provider about all the medicines you or your child take, includingprescription and over-the-counter medicines, vitamins, and herbal supplements.

Some of your other medicines may affect the way ELIQUIS works, causing side effects. Certain medicines may increase your risk of bleeding or stroke when taken with ELIQUIS. See “ What is the most important information I should know about ELIQUIS?”

Know the medicines you take. Keep a list of them to show your healthcare provider and pharmacist when you get a new medicine.

How should I take ELIQUIS?

- Take ELIQUIS exactly as prescribed by your healthcare provider.
- Take ELIQUIS 2 times every day.
- Do not change your dose or stop taking ELIQUIS unless your healthcare provider tells you to.
- If you or your child misses a dose of ELIQUIS, take it as soon as you remember on the same day. Do not take 2 doses of ELIQUIS at the same time to make up for a missed dose. Return to your usual dosing schedule the next day.
- For adults and children weighing at least 77 pounds (35 kg), if you have trouble swallowing the tablet whole, talk to your healthcare provider about other ways to take ELIQUIS tablets.
- Your healthcare provider will decide how long you should take ELIQUIS. Do not stop taking it without first talking with your healthcare provider.
- Do not run out of ELIQUIS. Refill your prescription before you run out.When leaving the hospital following hip or knee replacement, be sure that you will have ELIQUIS available to avoid missing any doses.
- If you take too much ELIQUIS, call your healthcare provider or go to the nearest hospital emergency room right away.
- Call your healthcare provider or healthcare provider right away if you fall or injure yourself, especially if you hit your head. Your healthcare provider or healthcare provider may need to check you.

For children who take ELIQUIS:

- See the detailed Instructions for Use that comes with ELIQUIS SPRINKLE for oral suspension or ELIQUIS tablets for oral suspension for information on how to prepare and give a dose of ELIQUISto children who weigh less than 77 pounds (35 kg) .
- Always give ELIQUIS exactly as your child’s healthcare provider or pharmacist has told you.
- The dose of ELIQUIS is based on your child’s body weight. Your child’s healthcare provider may need to change your child’s dose as their weight changes. Do not change your child’s dose without talking with the healthcare provider.
- If a child vomits or spits up within 30 minutes after taking ELIQUIS, repeat the dose. If a child vomits or spits up more than 30 minutes after taking ELIQUIS, do not repeat the dose. Continue to give the next ELIQUIS dose at the next scheduled time.
- Contact the healthcare provider if your child repeatedly vomits or spits up after taking ELIQUIS.

What are the possible side effects of ELIQUIS?

- See “What is the most important information I should know about ELIQUIS?”

The most common side effect of ELIQUIS in adults was bleeding.

The most common side effect of ELIQUIS in children include:

- headache

- heavy menstrual bleeding

- vomiting

These are not all of the possible side effects of ELIQUIS.

Call your doctor for medical advice about side effects. You may report side effects to FDA at 1-800-FDA-1088.

How should I store ELIQUIS?

Store ELIQUIS at room temperature between 68°F to 77°F (20°C to 25°C).

Keep ELIQUIS and all medicines out of the reach of children.

General Information about the safe and effective use of ELIQUIS.

Medicines are sometimes prescribed for purposes other than those listed in a Medication Guide. Do not use ELIQUIS for a condition for which it was not prescribed. Do not give ELIQUIS to other people, even if they have the same symptoms that you have. It may harm them. You can ask your pharmacist or healthcare provider for information about ELIQUIS that is written for health professionals.

What are the ingredients in ELIQUIS?

Active ingredient:apixaban

Inactive ingredients:

ELIQUIS tablets 2.5 mg and 5 mg: anhydrous lactose, croscarmellose sodium, magnesium stearate, microcrystalline cellulose, and sodium lauryl sulfate. The film coating contains hypromellose, lactose monohydrate, titanium dioxide, triacetin, and yellow iron oxide (2.5 mg tablets) or red iron oxide (5 mg tablets).

ELIQUIS 0.5 mg film coated tablets for oral suspension: anhydrous lactose, croscarmellose sodium, magnesium stearate, microcrystalline cellulose, sodium lauryl sulfate. The film coating contains hypromellose, lactose monohydrate, red iron oxide, titanium dioxide, and triacetin.

ELIQUIS SPRINKLE 0.15 mg for oral suspension: contains hypromellose and sugar spheres.

All other trademarks are property of their respective companies.

For more information, call 1-855-354-7847 (1-855-ELIQUIS) or go to www.ELIQUIS.com.

This Medication Guide has been approved by the U.S. Food and Drug Administration. | Revised 04/2025

Repackaged By / Distributed By: RemedyRepack Inc.

625 Kolter Drive, Indiana, PA 15701

(724) 465-8762

INSTRUCTIONS FOR USE

ELIQUIS®(ELL EH KWISS)
(APIXABAN)
TABLETS
FOR ORAL SUSPENSION

Important information you need to know before giving a dose of ELIQUIS tablets for oral suspension (ELIQUIS tablets):

- Read this Instructions for Use carefully before you prepare and give a dose of ELIQUIS tablets for the first time and each time you get a refill. There may be new information.
- This Instructions for Use does not take the place of talking with your healthcare provider about your child’s medical condition and treatment.
- Your healthcare provider or pharmacist should show you how to prepare and give a dose of ELIQUIS tablets. Always give this medicine exactly as your child’s healthcare provider or pharmacist has told you.
- If you have any questions about how to prepare or give a dose of ELIQUIS tablets, talk to the healthcare provider or pharmacist.
- Mix ELIQUIS tablets with food or liquid to give medicine. Do notswallow tablets.
- If given with liquid, give the medicine right away or within 2 hours of preparation.
- If given with food, give the medicine right away after preparation.
- If your child vomits or spits up within 30 minutes after taking ELIQUIS, repeat the dose. If your child vomits or spits up more than 30 minutes after taking ELIQUIS, do not repeat the dose.
- Contact the doctor if your child repeatedly vomits or spits up after taking ELIQUIS.
- For children who have difficulty swallowing, the liquid mixture can be delivered through a gastrostomy tube (G tube) or nasogastric tube (NG tube).
- For more information about ELIQUIS or if you have any questions, see the Medication Guide and talk with your healthcare provider.

Preparing the prescribed dose of ELIQUIS tablets

There are 2 ways you can mix and give ELIQUIS tablets:

- With liquidmethod, using an oral dosing syringe, or
- With foodmethod, using a small bowl and spoon.

You will need a medicine cup and oral dosing syringe (liquid mixing method) ora cup and small spoon (food mixing method) to give this medicine.

Liquid Mixing Method

❏ Step 1: Prepare Supplies

- Wash and dryyour hands.
- Clean and prepare a flat work surface.
- Gatheryour supplies:
- Packet(s)(check prescription label for the number of packet(s) needed for the prescribed dose).
- Oral dosing syringe (to give medicine to your child)
- Medicine cup (to mix medicine)
- Small spoon (to mix medicine)
- Small scissors (to open packet)
- Mixing liquid(use infant formula, water or apple juice).

You can ask your pharmacist for the oral dosing syringe and medicine cup.

Packet(s)

Small spoon
(not included)

Medicine cup
(not included)

Oral dosing syringe (not included)

Small scissors
(not included)

Mixing liquid (use infant
formula, water or apple juice)
(not included)

❏ Step 2: Check prescription label for prescribed dose

- Check the prescription label for the number of packet(s) needed for the prescribed dose.
- Repeat Step 3 and Step 4, if needed, to get the full prescribed dose.

❏ Step 3: Tap and open packet

- Tappacket to move the tablet(s) inside to the bottom.
- Cutthe dotted line on the packet to open it.

❏ Step 4: Empty the packet

- Emptythe tablet(s) inside the packet into the medicine cup.
- Runyour finger over the packet to remove all the tablet(s).

❏ Step 5: Add liquid to the medicine cup

- You will need 10 mL (2 teaspoons) of liquid total, regardless of the number of packets(s) prescribed.
- For children with fluid restrictions, your healthcare provider will tell you if you can use 2.5 mL of liquid.

Use water, infant formula, or apple juice only as the liquid. Do notuse any other type of liquid.

Important:To make sure your child gets the full dose, do notput the medicine in a baby bottle.

❏ Step 6: Mix medicine and liquid

- Holdthe medicine cup with one hand.
- Use a small spoon crush the tablet(s) and stir the medicine in the liquid.
- Continue to stir until tablet(s) are no longer visiblethroughout the liquid. This should take about 5 to 7 minutes.

5 to 7 minutes

❏ Step 7: Give oral suspension

This is a 2-part process to make sure all the medicine is given.

Follow Part 1 and Part 2.

Part 1: Pull up all liquid mixture with the oral dosing syringe and give all medicine in syringe.

Push plunger all the way down.

Place the syringe tip into the cup and pull up all the liquid mixture.

With the child seated upright or slightly inclined (tilted back), place the oral syringe into the mouth with the tip along either cheek.

Slowly push the plunger all the way down to give all medicine in the syringe.

Part 2: RepeatSteps 5 through 7 to give any remaining medicine in the cup:

Add about 5 mL (1 teaspoon) liquid to medicine cup.

For children with fluid restrictions, your healthcare provider will tell you if you can use 2.5 mL (½ teaspoon) of liquid.

Gently stir liquid with small spoon.

Push plunger all the way down.

Place the syringe tip into cup and pull up all the liquid mixture.

With the child seated upright or slightly inclined (tilted back), place the oral syringe into the mouth with the tip along either cheek.

Slowly push the plunger all the way down to give all medicine in the syringe.

❏ Step 8: Washing parts

- Throw away the empty packet(s) into the household trash.
- Remove the syringe plunger from the syringe barrel.
- Use only clean water to rinse the syringe parts, the medicine cup and small spoon.
- Put the syringe plunger back into the syringe barrel when dry.

Food Mixing Method

❏ Step 1: Prepare Supplies

- Wash and dryyour hands.
- Clean and prepare flat work surface.
- Gatheryour supplies:
- Packet(s)(check the prescription for the number of packet(s) needed for the prescribed dose).
- Small bowl (to mix medicine)
- Small spoon (to mix medicine)
- Small scissors (to open packet)
- Apple sauce

Packet(s)

Small spoon

(not included)

Small scissors (not included)

Apple sauce (not included)

Small bowl (not included)

❏ Step 2: Check prescription label for prescribed dose

- Check the prescription label for the number of packet(s) needed for the prescribed dose.
- Repeat Step 3 and Step 4, if needed, to get the full prescribed dose

❏ Step 3: Prepare for mixing

- Add approximately 15 mL (1 tablespoon)of applesauce to bowl.

❏ Step 4: Tap and open packet

- Tappacket to move the tablet(s) inside to the bottom.
- Cutthe dotted line on the packet to open it.

❏ Step 5: Empty the packet

- Emptythe tablet(s) inside the packet into the bowl.
- Runyour finger over the packet to remove all tablet(s).

❏ Step 6: Mix medicine and food

- Holdthe small bowl with one hand and use a small spoon to stir the tablet(s) into the apple sauce.

The tablet(s) do not need to disperse (evenly mix) in the food.

❏ Step 7: Give medicine

- With the child seated upright or slightly inclined (tilted back), givefood and medicine mixture by small spoon into the mouth
- Ensure all medicine and food have been given so no medicine is left in the bowl.

❏ Step 8: Washing parts

- Throwaway the empty packet(s) into the household trash.
- Washcup, small bowl and small spoon with soap and clean water. Let all items dry before next use.

Giving ELIQUIS tablets prepared as a suspension through a nasogastric tube (NG tube) or gastrostomy tube (G tube):

Follow steps 1 through 6 to prepare the dose to be given. Follow the manufacturer instructions for how to place the syringe tip into the tube and give the medicine to your child. After the medicine has been placed into the tube, using the syringe flush the tube with additional water or infant formula. The flush volume is shown in the table below.

Talk to your healthcare provider if you have any questions.

How should I store ELIQUIS tablets?

Store ELIQUIS at room temperature between 68°F to 77°F (20°C to 25°C).

Keep ELIQUIS and all medicines out of the reach of children.

All other trademarks are property of their respective companies.

For more information, call 1-855-354-7847 (1-855-ELIQUIS) or go to www.ELIQUIS.com.

This Instructions for Use has been approved by the U.S. Food and Drug Administration. | Issued: 04/2025

INSTRUCTIONS FOR USE

ELIQUIS®SPRINKLE (ELL EH KWISS SPRINK EL)
(APIXABAN)
FOR ORAL SUSPENSION

Important information you need to know before giving a dose of ELIQUIS SPRINKLE for oral suspension:

- Read this Instructions for Use carefully before you prepare and give a dose of ELIQUIS SPRINKLE for oral suspension for the first time and each time you get a refill. There may be new information.
- This Instructions for Use does not take the place of talking with your healthcare provider about your child’s medical condition and treatment.
- Your healthcare provider or pharmacist should show you how to prepare and give a dose of ELIQUIS SPRINKLE for oral suspension. Always give this medicine exactly as your child’s healthcare provider or pharmacist has told you.
- If you have any questions about how to prepare or give a dose of ELIQUIS SPRINKLE for oral suspension, talk to the healthcare provider or pharmacist.
- Open the capsule and sprinkle the entire contents of the capsule in water or infant formula.
- Do notswallow the capsule.
- Be sure to give the medicine right away or at the latest within 2 hours of preparation.
- If your child vomits or spits up within 30 minutes after taking ELIQUIS SPRINKLE, repeat the dose. If your child vomits or spits up more than 30 minutes after taking ELIQUIS SPRINKLE, do not repeat the dose.
- Contact the doctor if your child repeatedly vomits or spits up after taking ELIQUIS SPRINKLE.
- For more information about ELIQUIS SPRINKLE or if you have any questions, see the Medication Guide and talk with your healthcare provider.

PREPARING the prescribed DOSE of ELIQUIS SPRINKLE for oral suspension

❏ Step 1: Prepare Supplies

- Wash and dryyour hands.
- Clean and prepare a flat work surface.
- Gatheryour supplies:
- Oral dosing syringe (to give medicine to your child).
- Medicine cup (to mix medicine)
- Small spoon.
- Mixing liquid(use infant formula or water).

You can ask your pharmacist for the oral dosing syringe and medicine cup.

Capsule(s)

Mixing liquid (use infant formula or water) (not included)

Small spoon
(not included)

Medicine cup
(not included)

Oral dosing syringe (not included)

❏ Step 2: Check prescription label for number of capsules needed

- Repeat Step 3 and Step 4, if needed, to get the full prescribed dose.

❏ Step 3: Tap capsule

- Holdthe capsule with the colored end up.
- Tapthe clear end to get medicine into the clear end.

❏ Step 4: Open capsule

- Holdthe capsule over the medicine cup.
- Twistboth ends of the capsule and slowly pull it apart.
- Sprinklethe contents of the capsule into the medicine cup.
- Checkthe capsule shells to make sure they are empty.

Note: Do notswallow capsule.

1. Throw away (discard) capsule shells into the household trash.

❏ Step 5: Add liquid to the medicine cup

- You will need 5 mL (1 teaspoon) of liquid regardless of the number of capsule(s) prescribed.
- For children with fluid restrictions, your healthcare provider will tell you if you can use 2.5 mL of liquid.

Use water or infant formula only as the liquid. Do notuse any other type of liquid.

Important:To make sure your child gets the full dose, do notput the medicine in a baby bottle.

❏ Step 6: Mix medicine and liquid

- Holdthe medicine cup with one hand.
- Stirthe medicine in the liquid using a small spoon.
- Continue to stiruntil the powder particles can no longer be seen.

❏ Step 7: Give oral suspension

This is a 2-part process to make sure all the medicine is given.

Follow Part 1 and Part 2.

Part 1: Pull up all liquid mixture with the oral dosing syringe and give all medicine in syringe.

Push plunger all the way down.

Place the syringe tip into the cup and pull up all the liquid mixture.

With the child seated upright or slightly inclined (tilted back), place the oral syringe into the mouth with the tip along either cheek.

Slowly push the plunger all the way down to give all medicine in the syringe.

Part 2: RepeatSteps 5 through 7 to be certain you give any medicine remaining in the cup:

Add about 5 mL (1 teaspoon liquid to medicine cup.

For children with fluid restrictions, your healthcare provider will tell you if you can use 2.5 mL (½ teaspoon) of liquid .

Gently stir liquid with small spoon.

Push plunger all the way down.

Place the syringe tip into cup and pull up all the liquid mixture.

With the child seated upright or slightly inclined (tilted back), place the oral syringe into the mouth with the tip along either cheek.

Slowly push the plunger all the way down to give all medicine in the syringe.

❏ STEP 8: Washing parts

- Remove the syringe plunger from the syringe barrel.
- Use only clean water to rinse the syringe parts, the cup and spoon. Let all items dry before the next use.
- Put the syringe plunger back into the syringe barrel when dry.

How should I store ELIQUIS SPRINKLE for oral suspension?

Store ELIQUIS SPRINKLE at room temperature between 68°F to 77°F (20°C to 25°C).

Keep ELIQUIS SPRINKLE and all medicines out of the reach of children.

Marketed by:

Bristol-Myers Squibb Company Princeton, NJ 08543 USA

and

Pfizer Inc New York, NY 10001 USA

All other trademarks are property of their respective companies.

For more information, call 1-855-354-7847 (1-855-ELIQUIS) or go to www.ELIQUIS.com.

This Instructions for Use has been approved by the U.S. Food and Drug Administration. | Issued: 04/2025

PACKAGE LABEL

DRUG:

NDC: 70518-4462-0

PACKAGING: 30 in 1 BLISTER PACK

ACTIVE INGREDIENT(S):

apixaban

INACTIVE INGREDIENT(S):

anhydrous lactose (UNII: 3SY5LH9PMK)
MICROCRYSTALLINE CELLULOSE (UNII: OP1R32D61U)
croscarmellose sodium (UNII: M28OL1HH48)
sodium lauryl sulfate (UNII: 368GB5141J)
magnesium stearate (UNII: 70097M6I30)
lactose monohydrate (UNII: EWQ57Q8I5X)
HYPROMELLOSE, UNSPECIFIED (UNII: 3NXW29V3WO)
titanium dioxide (UNII: 15FIX9V2JP)
triacetin (UNII: XHX3C3X673)
ferric oxide yellow (UNII: EX438O2MRT)